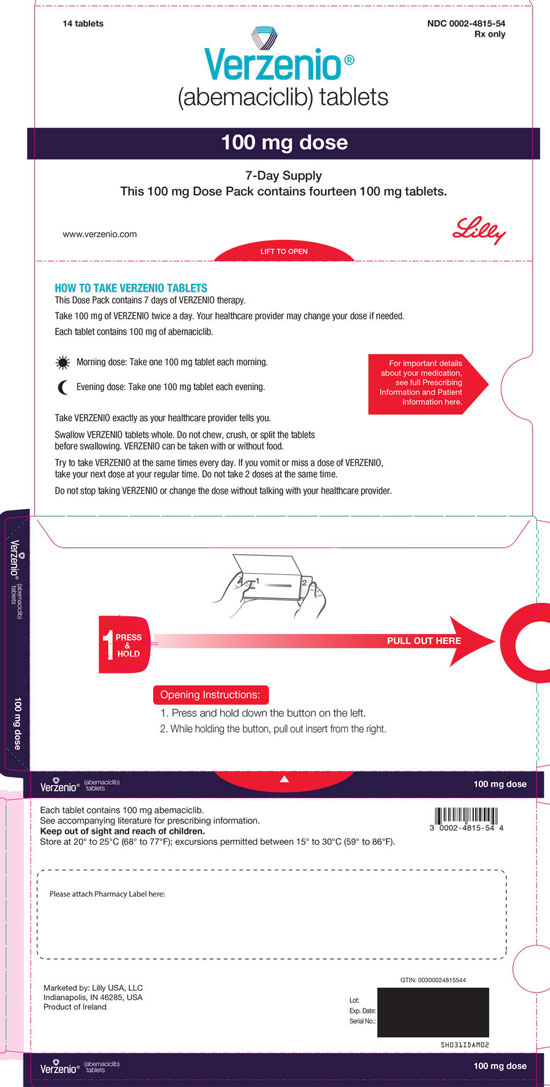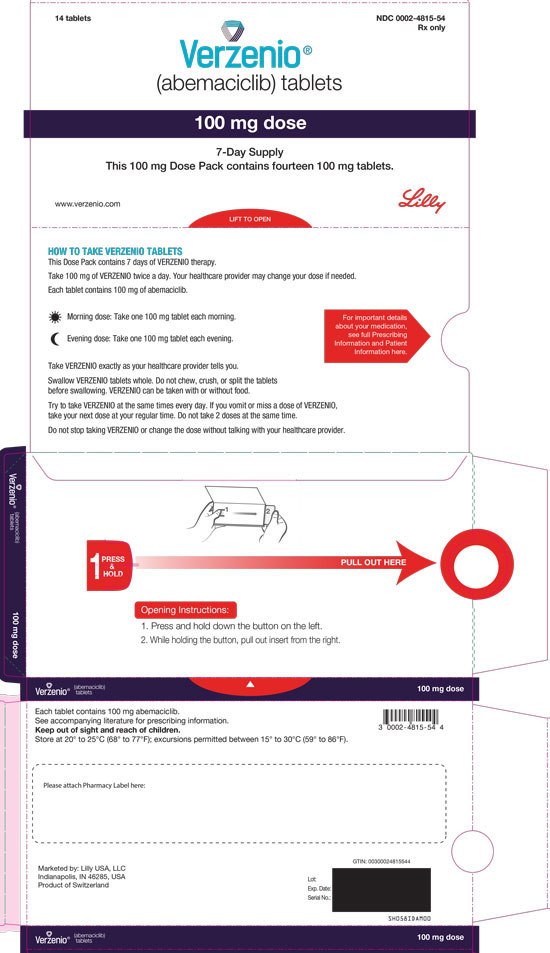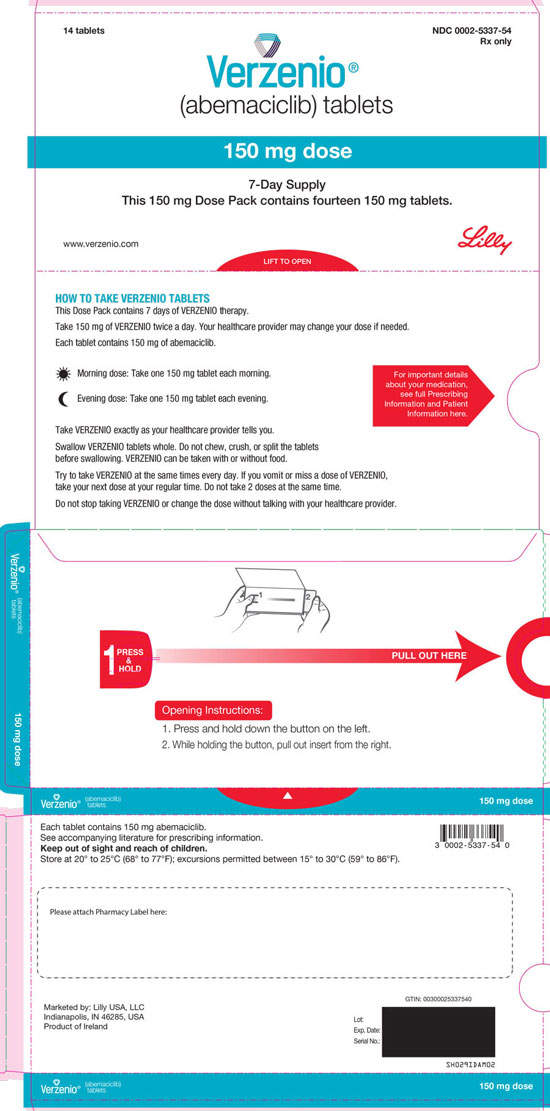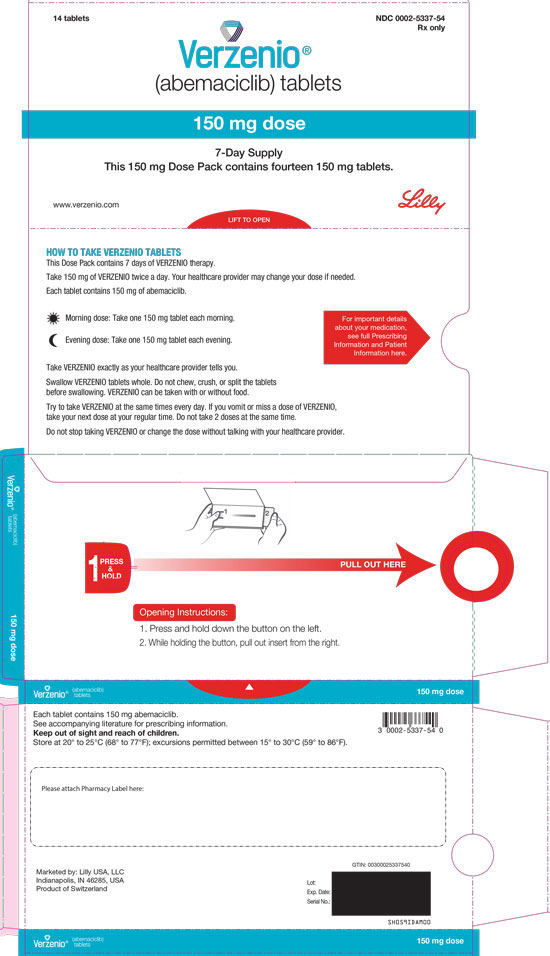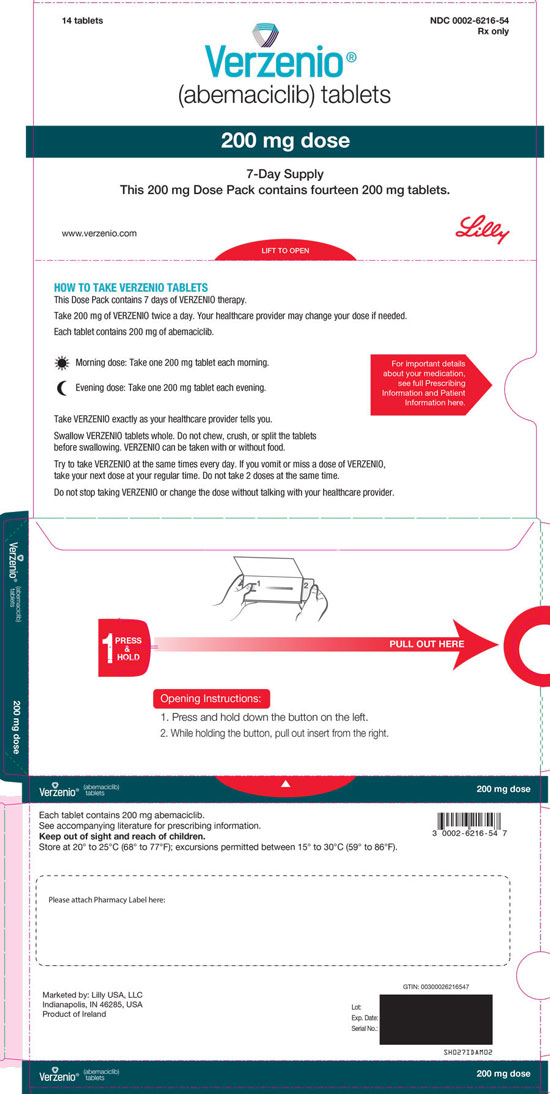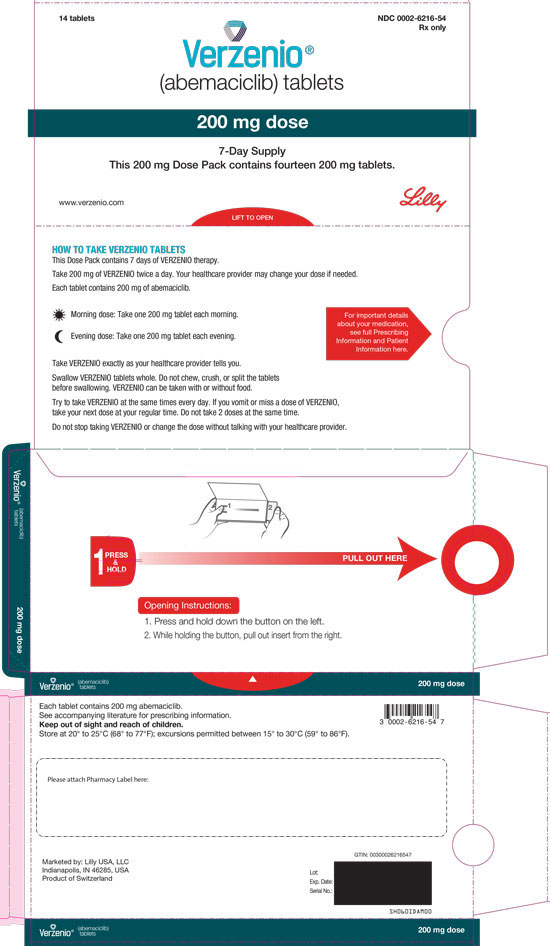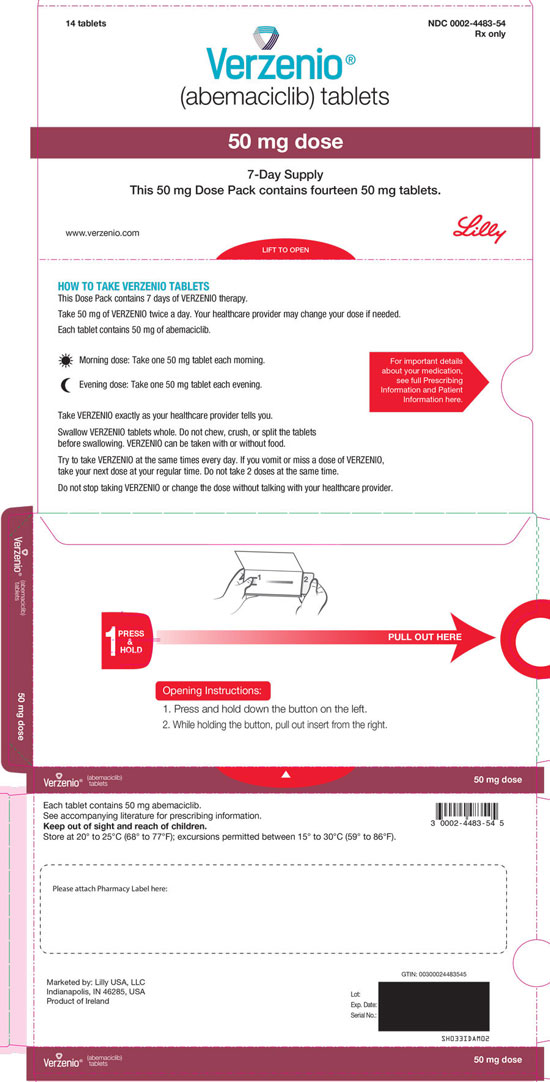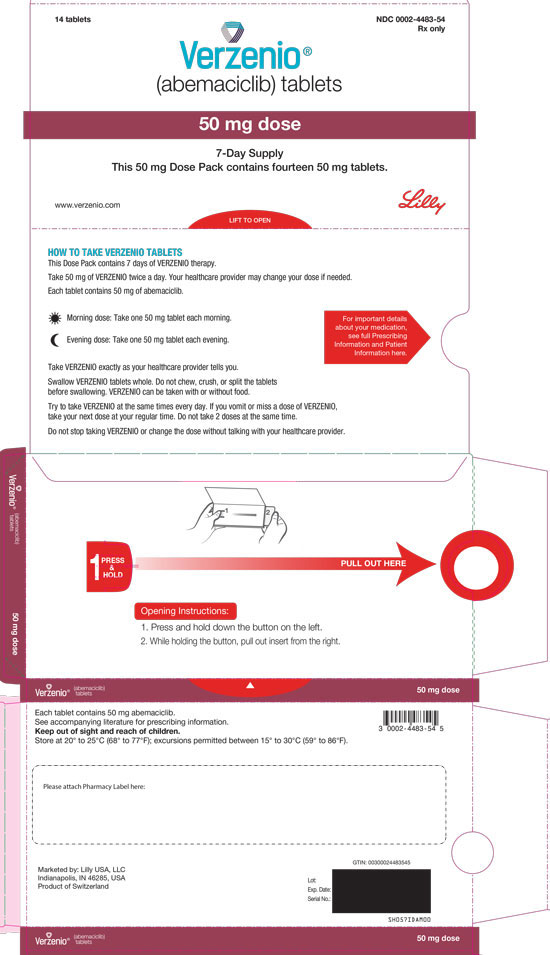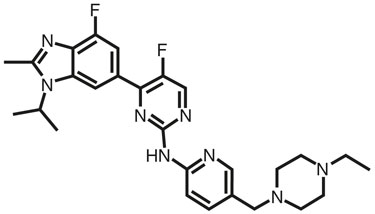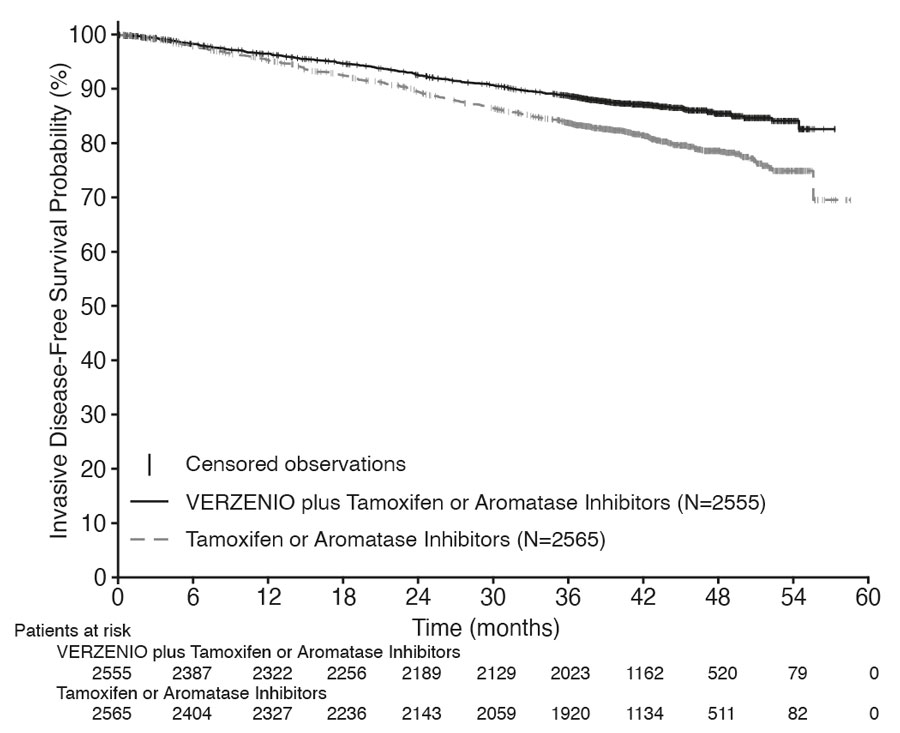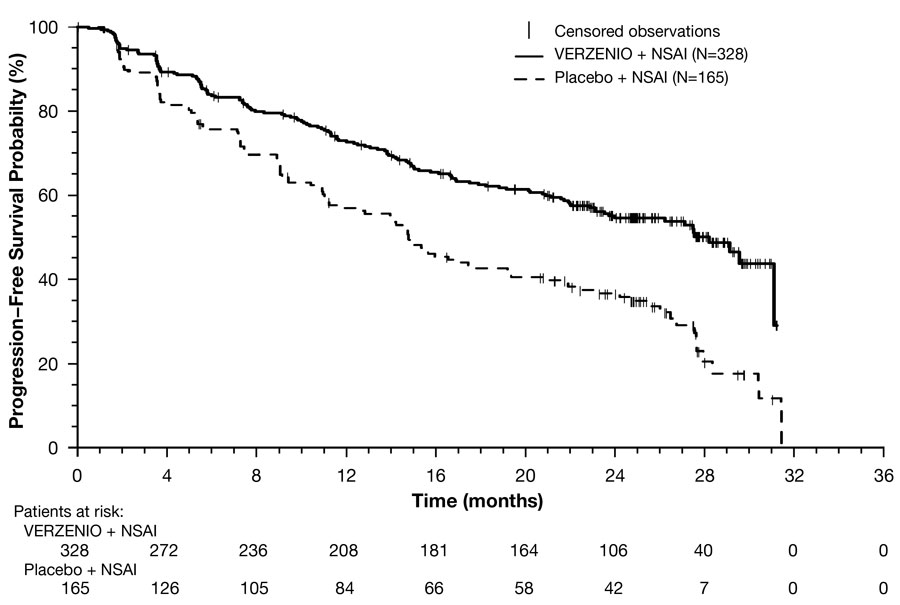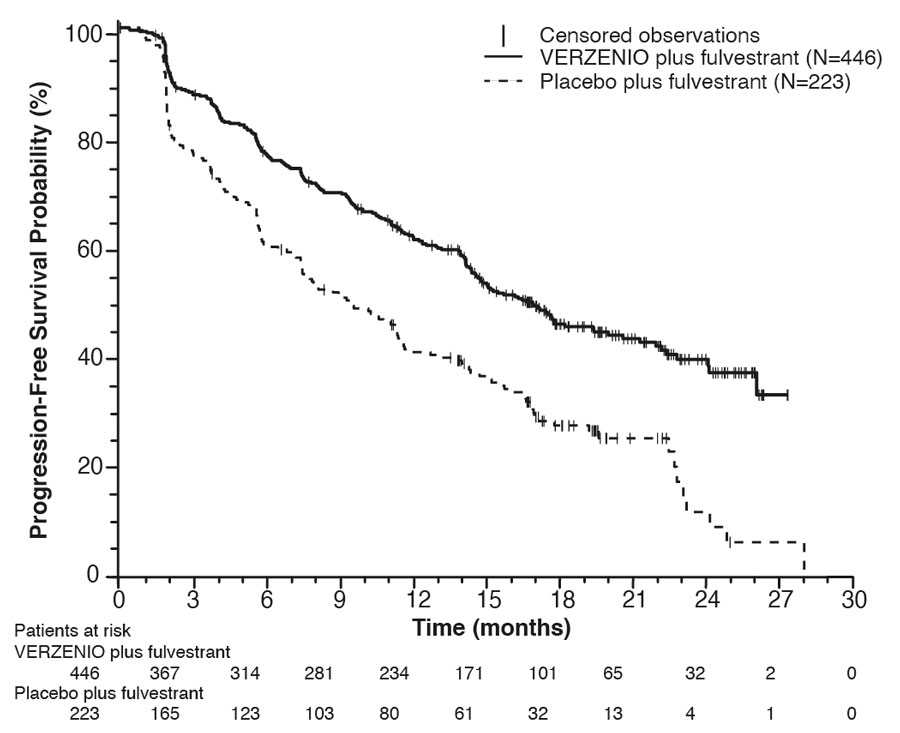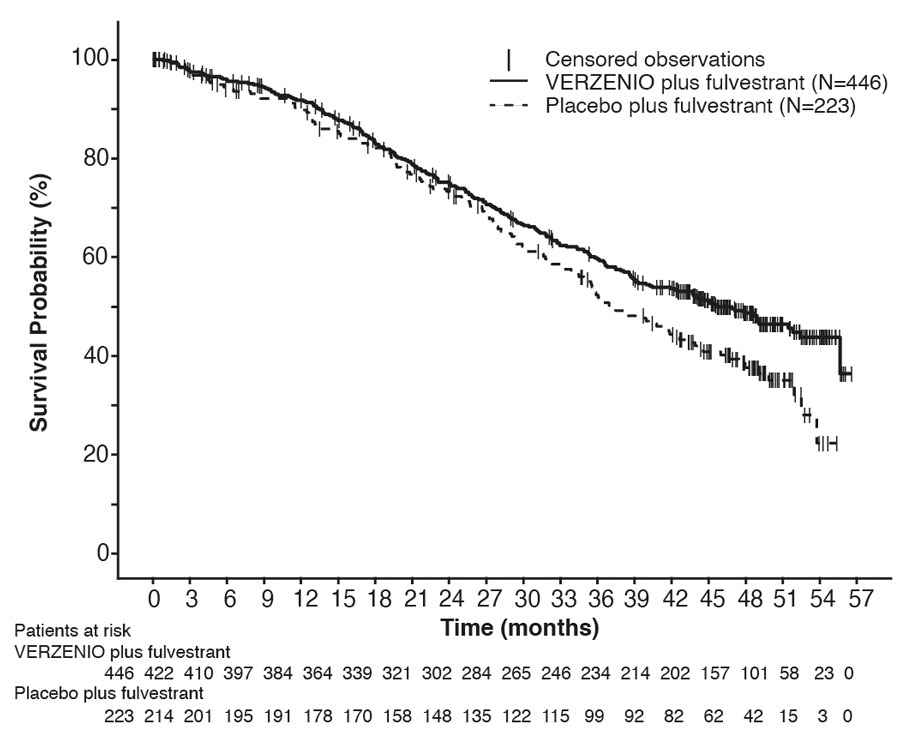 DRUG LABEL: Verzenio
NDC: 0002-4483 | Form: TABLET
Manufacturer: Eli Lilly and Company
Category: prescription | Type: HUMAN PRESCRIPTION DRUG LABEL
Date: 20250825

ACTIVE INGREDIENTS: abemaciclib 50 mg/1 1
INACTIVE INGREDIENTS: Microcrystalline Cellulose; Lactose Monohydrate; Croscarmellose Sodium; Silicon Dioxide; Sodium Stearyl Fumarate; Water; Polyvinyl Alcohol, Unspecified; Polyethylene Glycol, Unspecified; Titanium Dioxide; Talc; Ferric Oxide Yellow; Ferric Oxide Red

HIGHLIGHTS OF PRESCRIBING INFORMATION

These highlights do not include all the information needed to use VERZENIO safely and effectively. See full prescribing information for VERZENIO.
VERZENIO® (abemaciclib) tablets, for oral use
Initial U.S. Approval: 2017

1 INDICATIONS AND USAGE

VERZENIO® is a kinase inhibitor indicated:

- in combination with endocrine therapy (tamoxifen or an aromatase inhibitor) for the adjuvant treatment of adult patients with hormone receptor (HR)-positive, human epidermal growth factor receptor 2 (HER2)-negative, node-positive, early breast cancer at high risk of recurrence. (1.1, 14.1)
- in combination with an aromatase inhibitor as initial endocrine-based therapy for the treatment of adult patients with hormone receptor (HR)-positive, human epidermal growth factor receptor 2 (HER2)-negative advanced or metastatic breast cancer. (1.2)
- in combination with fulvestrant for the treatment of adult patients with hormone receptor (HR)-positive, human epidermal growth factor receptor 2 (HER2)-negative advanced or metastatic breast cancer with disease progression following endocrine therapy. (1.2)
- as monotherapy for the treatment of adult patients with HR-positive, HER2-negative advanced or metastatic breast cancer with disease progression following endocrine therapy and prior chemotherapy in the metastatic setting. (1.2)

2 DOSAGE AND ADMINISTRATION

VERZENIO tablets are taken orally with or without food. (2.1)

- Recommended starting dose in combination with fulvestrant, tamoxifen, or an aromatase inhibitor: 150 mg twice daily. (2.1)
- Recommended starting dose as monotherapy: 200 mg twice daily. (2.1)
- Dosing interruption and/or dose reductions may be required based on individual safety and tolerability. (2.2)

3 DOSAGE FORMS AND STRENGTHS

Tablets: 50 mg, 100 mg, 150 mg, and 200 mg. (3)

4 CONTRAINDICATIONS

None. (4)

5 WARNINGS AND PRECAUTIONS

- Diarrhea: VERZENIO can cause severe cases of diarrhea, associated with dehydration and infection. Instruct patients at the first sign of loose stools to initiate antidiarrheal therapy, increase oral fluids, and notify their healthcare provider. (2.2, 5.1)
- Neutropenia: Monitor complete blood counts prior to the start of VERZENIO therapy, every 2 weeks for the first 2 months, monthly for the next 2 months, and as clinically indicated. (2.2, 5.2)
- Interstitial Lung Disease (ILD)/Pneumonitis: Severe and fatal cases of ILD/pneumonitis have been reported. Monitor for clinical symptoms or radiological changes indicative of ILD/pneumonitis. Permanently discontinue VERZENIO in all patients with Grade 3 or 4 ILD or pneumonitis. (2.2, 5.3)
- Hepatotoxicity: Increases in serum transaminase levels have been observed. Perform liver function tests (LFTs) before initiating treatment with VERZENIO. Monitor LFTs every two weeks for the first two months, monthly for the next 2 months, and as clinically indicated. (2.2, 5.4)
- Venous Thromboembolism: Monitor patients for signs and symptoms of thrombosis and pulmonary embolism and treat as medically appropriate. (2.2, 5.5)
- Embryo-Fetal Toxicity: Can cause fetal harm. Advise patients of potential risk to a fetus and to use effective contraception. (5.6, 8.1, 8.3)

6 ADVERSE REACTIONS

Most common adverse reactions (incidence ≥20%) were diarrhea, neutropenia, nausea, abdominal pain, infections, fatigue, anemia, leukopenia, decreased appetite, vomiting, headache, alopecia, and thrombocytopenia. (6)

To report SUSPECTED ADVERSE REACTIONS, contact Eli Lilly and Company at 1-800-LillyRx (1-800-545-5979) or FDA at 1-800-FDA-1088 or www.fda.gov/medwatch.

7 DRUG INTERACTIONS

- CYP3A Inhibitors: Avoid concomitant use of ketoconazole. Reduce the VERZENIO dose with concomitant use of other strong and moderate CYP3A inhibitors. (2.2, 7.1)
- CYP3A Inducers: Avoid concomitant use of strong and moderate CYP3A inducers. (7.1)

8 USE IN SPECIFIC POPULATIONS

Lactation: Advise not to breastfeed. (8.2)

FULL PRESCRIBING INFORMATION

1 INDICATIONS AND USAGE

1.1 Early Breast Cancer

VERZENIO® (abemaciclib) is indicated:

- in combination with endocrine therapy (tamoxifen or an aromatase inhibitor) for the adjuvant treatment of adult patients with hormone receptor (HR)-positive, human epidermal growth factor receptor 2 (HER2)-negative, node-positive, early breast cancer at high risk of recurrence [see Clinical Studies (14.1)].

1.2 Advanced or Metastatic Breast Cancer

VERZENIO (abemaciclib) is indicated:

- in combination with an aromatase inhibitor as initial endocrine-based therapy for the treatment of adult patients with hormone receptor (HR)-positive, human epidermal growth factor receptor 2 (HER2)-negative advanced or metastatic breast cancer.
- in combination with fulvestrant for the treatment of adult patients with hormone receptor (HR)-positive, human epidermal growth factor receptor 2 (HER2)-negative advanced or metastatic breast cancer with disease progression following endocrine therapy.
- as monotherapy for the treatment of adult patients with HR-positive, HER2-negative advanced or metastatic breast cancer with disease progression following endocrine therapy and prior chemotherapy in the metastatic setting.

2 DOSAGE AND ADMINISTRATION

2.1 Recommended Dose and Schedule

- When used in combination with fulvestrant, tamoxifen, or an aromatase inhibitor, the recommended dose of VERZENIO is 150 mg taken orally twice daily. Refer to the Full Prescribing Information for the recommended dose of the fulvestrant, tamoxifen, or aromatase inhibitor being used.
- Pre/perimenopausal women and men treated with the combination of VERZENIO plus an aromatase inhibitor should be treated with a gonadotropin-releasing hormone agonist (GnRH) according to current clinical practice standards.
- Pre/perimenopausal women treated with the combination of VERZENIO plus fulvestrant should be treated with a GnRH according to current clinical practice standards
- When used as monotherapy, the recommended dose of VERZENIO is 200 mg taken orally twice daily.
- For early breast cancer, continue VERZENIO until completion of 2 years of treatment or until disease recurrence, or unacceptable toxicity.
- For advanced or metastatic breast cancer, continue treatment until disease progression or unacceptable toxicity.

VERZENIO may be taken with or without food [see Clinical Pharmacology (12.3)].

Instruct patients to take their doses of VERZENIO at approximately the same times every day.

If the patient vomits or misses a dose of VERZENIO, instruct the patient to take the next dose at its scheduled time. Instruct patients to swallow VERZENIO tablets whole and not to chew, crush, or split tablets before swallowing. Instruct patients not to ingest VERZENIO tablets if broken, cracked, or otherwise not intact.

2.2 Dose Modification

Dose Modifications for Adverse Reactions

The recommended VERZENIO dose modifications for adverse reactions are provided in Tables 1-7. Discontinue VERZENIO for patients unable to tolerate 50 mg twice daily.

Table 1: VERZENIO Dose Modification — Adverse Reactions
Dose Level | VERZENIO Dose Combination with Fulvestrant, Tamoxifen, or an Aromatase Inhibitor | VERZENIO Dose for Monotherapy
Recommended starting dose | 150 mg twice daily | 200 mg twice daily
First dose reduction | 100 mg twice daily | 150 mg twice daily
Second dose reduction | 50 mg twice daily | 100 mg twice daily
Third dose reduction | not applicable | 50 mg twice daily

Table 2: VERZENIO Dose Modification and Management — Hematologic Toxicitiesa
Monitor complete blood counts prior to the start of VERZENIO therapy, every 2 weeks for the first 2 months, monthly for the next 2 months, and as clinically indicated.
CTCAE Grade | VERZENIO Dose Modifications
Grade 1 or 2 | No dose modification is required.
Grade 3 | Suspend dose until toxicity resolves to ≤Grade 2. Dose reduction is not required.
Grade 3 recurrent, or Grade 4 | Suspend dose until toxicity resolves to ≤Grade 2. Resume at next lower dose.
Abbreviation: CTCAE = Common Terminology Criteria for Adverse Events.
a If blood cell growth factors are required, suspend VERZENIO dose for at least 48 hours after the last dose of blood cell growth factor and until toxicity resolves to ≤Grade 2. Resume at next lower dose unless already performed for the toxicity that led to the use of the growth factor. Growth factor use as per current treatment guidelines.

Table 3: VERZENIO Dose Modification and Management — Diarrhea
At the first sign of loose stools, start treatment with antidiarrheal agents and increase intake of oral fluids.
CTCAE Grade | VERZENIO Dose Modifications
Grade 1 | No dose modification is required.
Grade 2 | If toxicity does not resolve within 24 hours to ≤Grade 1, suspend dose until resolution. No dose reduction is required.
Grade 2 that persists or recurs after resuming the same dose despite maximal supportive measures | Suspend dose until toxicity resolves to ≤Grade 1. Resume at next lower dose.
Grade 3 or 4 or requires hospitalization | Suspend dose until toxicity resolves to ≤Grade 1. Resume at next lower dose.

Table 4: VERZENIO Dose Modification and Management — Hepatotoxicity
Monitor ALT, AST, and serum bilirubin prior to the start of VERZENIO therapy, every 2 weeks for the first 2 months, monthly for the next 2 months, and as clinically indicated.
CTCAE Grade for ALT and AST | VERZENIO Dose Modifications
Grade 1 (>ULN-3.0 x ULN) Grade 2 (>3.0-5.0 x ULN), WITHOUT increase in total bilirubin above 2 x ULN | No dose modification is required.
Persistent or Recurrent Grade 2, or Grade 3 (>5.0-20.0 x ULN), WITHOUT increase in total bilirubin above 2 x ULN | Suspend dose until toxicity resolves to baseline or Grade 1. Resume at next lower dose.
Elevation in AST and/or ALT >3 x ULN WITH total bilirubin >2 x ULN, in the absence of cholestasis | Discontinue VERZENIO.
Grade 4 (>20.0 x ULN) | Discontinue VERZENIO.
Abbreviations: ALT = alanine aminotransferase, AST = aspartate aminotransferase, ULN = upper limit of normal.

Table 5: VERZENIO Dose Modification and Management — Interstitial Lung Disease/Pneumonitis
CTCAE Grade | VERZENIO Dose Modifications
Grade 1 or 2 | No dose modification is required.
Persistent or recurrent Grade 2 toxicity that does not resolve with maximal supportive measures within 7 days to baseline or Grade 1 | Suspend dose until toxicity resolves to baseline or ≤Grade 1. Resume at next lower dose.
Grade 3 or 4 | Discontinue VERZENIO.

Table 6: VERZENIO Dose Modification and Management — Venous Thromboembolic Events (VTEs)
CTCAE Grade | VERZENIO Dose Modifications
Early Breast Cancer
Any Grade | Suspend dose and treat as clinically indicated. Resume VERZENIO when the patient is clinically stable.
Advanced or Metastatic Breast Cancer
Grade 1 or 2 | No dose modification is required.
Grade 3 or 4 | Suspend dose and treat as clinically indicated. Resume VERZENIO when the patient is clinically stable.

Table 7: VERZENIO Dose Modification and Management — Other Toxicitiesa
CTCAE Grade | VERZENIO Dose Modifications
Grade 1 or 2 | No dose modification is required.
Persistent or recurrent Grade 2 toxicity that does not resolve with maximal supportive measures within 7 days to baseline or Grade 1 | Suspend dose until toxicity resolves to baseline or ≤Grade 1. Resume at next lower dose.
Grade 3 or 4 | Suspend dose until toxicity resolves to baseline or ≤Grade 1. Resume at next lower dose.
a Excluding diarrhea, hematologic toxicity, hepatotoxicity, ILD/pneumonitis, and VTEs.

Refer to the Full Prescribing Information for coadministered fulvestrant, tamoxifen, or an aromatase inhibitor for dose modifications and other relevant safety information.

Dose Modification for Use with Strong and Moderate CYP3A Inhibitors

Avoid concomitant use of the strong CYP3A inhibitor ketoconazole.

With concomitant use of strong CYP3A inhibitors other than ketoconazole, in patients with recommended starting doses of 200 mg twice daily or 150 mg twice daily, reduce the VERZENIO dose to 100 mg twice daily. In patients who have had a dose reduction to 100 mg twice daily due to adverse reactions, further reduce the VERZENIO dose to 50 mg twice daily. If a patient taking VERZENIO discontinues a CYP3A inhibitor, increase the VERZENIO dose (after 3-5 half-lives of the inhibitor) to the dose that was used before starting the strong inhibitor [see Drug Interactions (7.1) and Clinical Pharmacology (12.3)].

With concomitant use of moderate CYP3A inhibitors, monitor for adverse reactions and consider reducing the VERZENIO dose in 50 mg decrements as demonstrated in Table 1, if necessary.

Dose Modification for Patients with Severe Hepatic Impairment

For patients with severe hepatic impairment (Child Pugh-C), reduce the VERZENIO dosing frequency to once daily [see Use in Specific Populations (8.7) and Clinical Pharmacology (12.3)].

Refer to the Full Prescribing Information for the coadministered fulvestrant, tamoxifen, or aromatase inhibitor for dose modification requirements for severe hepatic impairment.

3 DOSAGE FORMS AND STRENGTHS

50 mg tablets: oval beige tablet with “Lilly” debossed on one side and “50” on the other side.

100 mg tablets: oval white to practically white tablet with “Lilly” debossed on one side and “100” on the other side.

150 mg tablets: oval yellow tablet with “Lilly” debossed on one side and “150” on the other side.

200 mg tablets: oval beige tablet with “Lilly” debossed on one side and “200” on the other side.

4 CONTRAINDICATIONS

None.

5 WARNINGS AND PRECAUTIONS

5.1 Diarrhea

Severe diarrhea associated with dehydration and infection occurred in patients treated with VERZENIO.

Across four clinical trials in 3691 patients, diarrhea occurred in 81% to 90% of patients who received VERZENIO. Grade 3 diarrhea occurred in 8% to 20% of patients receiving VERZENIO [see Adverse Reactions (6.1)].

Most patients experienced diarrhea during the first month of VERZENIO treatment. The median time to onset of the first diarrhea event ranged from 6 to 8 days; and the median duration of Grade 2 and Grade 3 diarrhea ranged from 6 to 11 days and 5 to 8 days, respectively. Across trials, 19% to 26% of patients with diarrhea required a VERZENIO dose interruption and 13% to 23% required a dose reduction.

Instruct patients to start antidiarrheal therapy such as loperamide at the first sign of loose stools, increase oral fluids, and notify their healthcare provider for further instructions and appropriate follow up [see Patient Counseling Information (17)]. For Grade 3 or 4 diarrhea, or diarrhea that requires hospitalization, discontinue VERZENIO until toxicity resolves to ≤Grade 1, and then resume VERZENIO at the next lower dose [see Dosage and Administration (2.2)].

5.2 Neutropenia

Neutropenia, including febrile neutropenia and fatal neutropenic sepsis, occurred in patients treated with VERZENIO.

Across four clinical trials in 3691 patients, neutropenia occurred in a 37% to 46% of patients receiving VERZENIO. A Grade ≥3 decrease in neutrophil count (based on laboratory findings) occurred in 19% to 32% of patients receiving VERZENIO. Across trials, the median time to the first episode of Grade ≥3 neutropenia ranged from 29 days to 33 days, and the median duration of Grade ≥3 neutropenia ranged from 11 days to 16 days [see Adverse Reactions (6.1)].

Febrile neutropenia has been reported in <1% of patients exposed to VERZENIO across trials. Two deaths due to neutropenic sepsis were observed in MONARCH 2. Inform patients to promptly report any episodes of fever to their healthcare provider [see Patient Counseling Information (17)].

Monitor complete blood counts prior to the start of VERZENIO therapy, every 2 weeks for the first 2 months, monthly for the next 2 months, and as clinically indicated. Dose interruption, dose reduction, or delay in starting treatment cycles is recommended for patients who develop Grade 3 or 4 neutropenia [see Dosage and Administration (2.2)].

5.3 Interstitial Lung Disease (ILD) or Pneumonitis

Severe, life-threatening, or fatal interstitial lung disease (ILD) or pneumonitis can occur in patients treated with VERZENIO and other CDK4/6 inhibitors. In VERZENIO-treated patients in early breast cancer (monarchE, N=2791), 3% of patients experienced ILD or pneumonitis of any grade: 0.4% were Grade 3 or 4 and there was one fatality (0.1%). In VERZENIO-treated patients in advanced or metastatic breast cancer (N=900) (MONARCH 1, MONARCH 2, MONARCH 3), 3.3% of VERZENIO-treated patients had ILD or pneumonitis of any grade: 0.6% had Grade 3 or 4, and 0.4% had fatal outcomes. Additional cases of ILD or pneumonitis have been observed in the postmarketing setting, with fatalities reported [see Adverse Reactions (6.2)].

Monitor patients for pulmonary symptoms indicative of ILD or pneumonitis. Symptoms may include hypoxia, cough, dyspnea, or interstitial infiltrates on radiologic exams. Infectious, neoplastic, and other causes for such symptoms should be excluded by means of appropriate investigations.

Dose interruption or dose reduction is recommended for patients who develop persistent or recurrent Grade 2 ILD or pneumonitis. Permanently discontinue VERZENIO in all patients with Grade 3 or 4 ILD or pneumonitis [see Dosage and Administration (2.2)].

5.4 Hepatotoxicity

Grade ≥3 ALT (2% to 6%) and AST (2% to 3%) were reported in patients receiving VERZENIO.

Across three clinical trials in 3559 patients (monarchE, MONARCH 2, MONARCH 3), the median time to onset of Grade ≥3 ALT increases ranged from 57 to 87 days and the median time to resolution to Grade <3 was 13 to 14 days. The median time to onset of Grade ≥3 AST increases ranged from 71 to 185 days and the median time to resolution to Grade <3 ranged from 11 to 15 days.

Monitor liver function tests (LFTs) prior to the start of VERZENIO therapy, every 2 weeks for the first 2 months, monthly for the next 2 months, and as clinically indicated. Dose interruption, dose reduction, dose discontinuation, or delay in starting treatment cycles is recommended for patients who develop persistent or recurrent Grade 2, or any Grade 3 or Grade 4 hepatic transaminase elevation [see Dosage and Administration (2.2)].

5.5 Venous Thromboembolism

Across three clinical trials in 3559 patients (monarchE, MONARCH 2, MONARCH 3), venous thromboembolic events were reported in 2% to 5% of patients treated with VERZENIO. Venous thromboembolic events included deep vein thrombosis, pulmonary embolism, pelvic venous thrombosis, cerebral venous sinus thrombosis, subclavian and axillary vein thrombosis, and inferior vena cava thrombosis. In clinical trials, deaths due to venous thromboembolism have been reported in patients treated with VERZENIO.

VERZENIO has not been studied in patients with early breast cancer who had a history of venous thromboembolism. Monitor patients for signs and symptoms of venous thrombosis and pulmonary embolism and treat as medically appropriate. Dose interruption is recommended for early breast cancer patients with any grade venous thromboembolic event and for advanced or metastatic breast cancer patients with a Grade 3 or 4 venous thromboembolic event [see Dosage and Administration (2.2)].

5.6 Embryo-Fetal Toxicity

Based on findings from animal studies and the mechanism of action, VERZENIO can cause fetal harm when administered to a pregnant woman. In animal reproduction studies, administration of abemaciclib to pregnant rats during the period of organogenesis caused teratogenicity and decreased fetal weight at maternal exposures that were similar to the human clinical exposure based on area under the curve (AUC) at the maximum recommended human dose.

Advise pregnant women of the potential risk to a fetus. Advise females of reproductive potential to use effective contraception during treatment with VERZENIO and for 3 weeks after the last dose [see Use in Specific Populations (8.1, 8.3) and Clinical Pharmacology (12.1)].

6 ADVERSE REACTIONS

The following adverse reactions are discussed in greater detail in other sections of the labeling:

- Diarrhea [see Warnings and Precautions (5.1)].
- Neutropenia [see Warnings and Precautions (5.2)].
- Interstitial Lung Disease (ILD) or Pneumonitis [see Warnings and Precautions (5.3)].
- Hepatotoxicity [see Warnings and Precautions (5.4)].
- Venous Thromboembolism [see Warnings and Precautions (5.5)].

6.1 Clinical Studies Experience

Because clinical trials are conducted under widely varying conditions, adverse reaction rates observed in the clinical trials of a drug cannot be directly compared to rates in the clinical trials of another drug and may not reflect the rates observed in practice.

The safety population described in the Warnings and Precautions reflect exposure to VERZENIO in 3691 patients from four clinical trials: monarchE, MONARCH 1, MONARCH 2, and MONARCH 3. The safety population includes exposure to VERZENIO as a single agent at 200 mg twice daily in 132 patients in MONARCH 1 and to VERZENIO at 150 mg twice daily in 3559 patients administered in combination with fulvestrant, tamoxifen, or an aromatase inhibitor in monarchE, MONARCH 2, and MONARCH 3. The median duration of exposure ranged from 4.5 months in MONARCH 1 to 24 months in monarchE. The most common adverse reactions (incidence ≥20%) across clinical trials were: diarrhea, neutropenia, nausea, abdominal pain, infections, fatigue, anemia, leukopenia, decreased appetite, vomiting, headache, alopecia, and thrombocytopenia.

Early Breast Cancer

monarchE: VERZENIO in Combination with Tamoxifen or an Aromatase Inhibitor as Adjuvant Treatment

Adult patients with HR-positive, HER2-negative, node-positive early breast cancer at a high risk of recurrence

The safety of VERZENIO was evaluated in monarchE, a study of 5591 adult patients receiving VERZENIO plus endocrine therapy (tamoxifen or an aromatase inhibitor) or endocrine therapy (tamoxifen or an aromatase inhibitor) alone [see Clinical Studies (14.1)]. Patients were randomly assigned to receive 150 mg of VERZENIO orally, twice daily, plus tamoxifen or an aromatase inhibitor, or tamoxifen or an aromatase inhibitor, for two years or until discontinuation criteria were met. The median duration of VERZENIO treatment was 24 months.

The most frequently reported (≥5%) Grade 3 or 4 adverse reactions were neutropenia, leukopenia, diarrhea, and lymphopenia.

Fatal adverse reactions occurred in 0.8% of patients who received VERZENIO plus endocrine therapy (tamoxifen or an aromatase inhibitor), including: cardiac failure (0.1%), cardiac arrest, myocardial infarction, ventricular fibrillation, cerebral hemorrhage, cerebrovascular accident, pneumonitis, hypoxia, diarrhea, and mesenteric artery thrombosis (0.03% each).

Permanent VERZENIO treatment discontinuation due to an adverse reaction was reported in 19% of patients receiving VERZENIO, plus tamoxifen or an aromatase inhibitor. Of the patients receiving tamoxifen or an aromatase inhibitor, 1% permanently discontinued due to an adverse reaction. The most common adverse reactions leading to VERZENIO discontinuations were diarrhea (5%), fatigue (2%), and neutropenia (0.9%).

Dose interruption of VERZENIO due to an adverse reaction occurred in 62% of patients receiving VERZENIO plus tamoxifen or aromatase inhibitors. Adverse reactions leading to VERZENIO dose interruptions in ≥5% of patients were diarrhea (20%), neutropenia (16%), leukopenia (7%), and fatigue (5%).

Dose reductions of VERZENIO due to an adverse reaction occurred in 44% of patients receiving VERZENIO plus endocrine therapy (tamoxifen or an aromatase inhibitor). Adverse reactions leading to VERZENIO dose reductions in ≥5% were diarrhea (17%), neutropenia (8%), and fatigue (5%).

The most common adverse reactions reported (≥20%) in the VERZENIO, plus tamoxifen or an aromatase inhibitor, arm and ≥2% higher than the tamoxifen or an aromatase inhibitor arm were: diarrhea, infections, neutropenia, fatigue, leukopenia, nausea, anemia, and headache. Adverse reactions are shown in Table 8 and laboratory abnormalities are shown in Table 9.

Table 8: Adverse Reactions (≥10%) of Patients Receiving VERZENIO Plus Tamoxifen or an Aromatase Inhibitor [with a Difference between Arms of ≥2%] in monarchE
 | VERZENIO Plus Tamoxifen or an Aromatase Inhibitor N=2791 |  |  | Tamoxifen or an Aromatase Inhibitor N=2800
 | All Gradesa % | Grade 3 % | Grade 4 % | All Gradesb % | Grade 3 % | Grade 4 %
Gastrointestinal Disorders
Diarrhea | 84 | 8 | 0 | 9 | 0.2 | 0
Nausea | 30 | 0.5 | 0 | 9 | <0.1 | 0
Vomiting | 18 | 0.5 | 0 | 4.6 | 0.1 | 0
Stomatitisc | 14 | 0.1 | 0 | 5 | 0 | 0
Infections and Infestations
Infectionsd | 51 | 4.9 | 0.6 | 39 | 2.7 | 0.1
General Disorders and Administration Site Conditions
Fatiguee | 41 | 2.9 | 0 | 18 | 0.1 | 0
Nervous System Disorders
Headache | 20 | 0.3 | 0 | 15 | 0.2 | 0
Dizziness | 11 | 0.1 | 0 | 7 | <0.1 | 0
Metabolism and Nutrition Disorders
Decreased appetite | 12 | 0.6 | 0 | 2.4 | <0.1 | 0
Skin and Subcutaneous Tissue Disorders
Rashf | 11 | 0.4 | 0 | 4.5 | 0 | 0
Alopecia | 11 | 0 | 0 | 2.7 | 0 | 0
a Includes the following fatal adverse reactions: diarrhea (n=1), and infections (n=4)
b Includes the following fatal adverse reactions: infections (n=5)
c Includes mouth ulceration, mucosal inflammation, oropharyngeal pain, stomatitis.
d Includes all reported preferred terms that are part of the Infections and Infestations system organ class. Most common infections (>5%) include upper respiratory tract infection, urinary tract infection, and nasopharyngitis.
e Includes asthenia, fatigue.
f Includes exfoliative rash, mucocutaneous rash, rash, rash erythematous, rash follicular, rash generalized, rash macular, rash maculo-papular, rash maculovesicular, rash morbilliform, rash papular, rash papulosquamous, rash pruritic, rash vesicular, vulvovaginal rash.

Clinically relevant adverse reactions in <10% of patients who received VERZENIO in combination with tamoxifen or an aromatase inhibitor in monarchE include:

- Pruritus-9%
- Dyspepsia-8%
- Nail disorder-6% (includes nail bed disorder, nail bed inflammation, nail discoloration, nail disorder, nail dystrophy, nail pigmentation, nail ridging, nail toxicity, onychalgia, onychoclasis, onycholysis, onychomadesis)
- Lacrimation increased-6%
- Dysgeusia-5%
- Interstitial lung disease (ILD)/pneumonitis-3% (includes pneumonitis, radiation pneumonitis, interstitial lung disease, pulmonary fibrosis, organizing pneumonia, radiation fibrosis – lung, lung opacity, sarcoidosis)
- Venous thromboembolic events (VTEs)-3% (includes catheter site thrombosis, cerebral venous thrombosis, deep vein thrombosis, device related thrombosis, embolism, hepatic vein thrombosis, jugular vein occlusion, jugular vein thrombosis, ovarian vein thrombosis, portal vein thrombosis, pulmonary embolism, subclavian vein thrombosis, venous thrombosis limb)

Table 9: Laboratory Abnormalities (≥10%) in Patients Receiving VERZENIO Plus Tamoxifen or an Aromatase Inhibitor [with a Difference between Arms of ≥2%] in monarchE
 | VERZENIO Plus Tamoxifen or an Aromatase Inhibitor N=2791 |  |  | Tamoxifen or an Aromatase Inhibitor N=2800
 | All Grades % | Grade 3 % | Grade 4 % | All Grades % | Grade 3 % | Grade 4 %
Creatinine increased | 99 | 0.5 | 0 | 91 | <0.1 | 0
White blood cell decreased | 89 | 19 | <0.1 | 28 | 1.1 | 0
Neutrophil count decreased | 84 | 18 | 0.7 | 23 | 1.6 | 0.3
Anemia | 68 | 1.0 | 0 | 17 | 0.1 | 0
Lymphocyte count decreased | 59 | 13 | 0.2 | 24 | 2.4 | 0.1
Platelet count decreased | 37 | 0.7 | 0.2 | 10 | 0.1 | 0.1
Alanine aminotransferase increased | 37 | 2.5 | <0.1 | 24 | 1.2 | 0
Aspartate aminotransferase increased | 31 | 1.5 | <0.1 | 18 | 0.9 | 0
Hypokalemia | 11 | 1.2 | 0.1 | 3.8 | 0.1 | 0.1

Advanced or Metastatic Breast Cancer

MONARCH 3: VERZENIO in Combination with an Aromatase Inhibitor (Anastrozole or Letrozole) as Initial Endocrine-Based Therapy

Postmenopausal Women with HR-positive, HER2-negative locoregionally recurrent or metastatic breast cancer with no prior systemic therapy in this disease setting

The safety of VERZENIO was evaluated in MONARCH 3, a study of 488 women receiving VERZENIO plus an aromatase inhibitor or placebo plus an aromatase inhibitor [see Clinical Studies (14.2)]. Patients were randomly assigned to receive 150 mg of VERZENIO or placebo orally twice daily, plus physician's choice of anastrozole or letrozole once daily. Median duration of treatment was 15.1 months for the VERZENIO arm and 13.9 months for the placebo arm.

The most frequently reported (≥5%) Grade 3 or 4 adverse reactions were neutropenia, diarrhea, leukopenia, increased ALT, and anemia.

Deaths during treatment or during the 30-day follow up, regardless of causality, were reported in 11 cases (3%) of VERZENIO plus an aromatase inhibitor treated patients versus 3 cases (2%) of placebo plus an aromatase inhibitor treated patients. Causes of death for patients receiving VERZENIO plus an aromatase inhibitor included: 3 (0.9%) patient deaths due to underlying disease, 3 (0.9%) due to lung infection, 3 (0.9%) due to VTE, 1 (0.3%) due to pneumonitis, and 1 (0.3%) due to cerebral infarction.

Permanent treatment discontinuation due to an adverse reaction was reported in 13% of patients receiving VERZENIO plus an aromatase inhibitor and in 3% of patients receiving placebo plus an aromatase inhibitor. Adverse reactions leading to permanent discontinuation for patients receiving VERZENIO plus an aromatase inhibitor were diarrhea (2%), ALT increased (2%), infection (1%), venous thromboembolic events (VTE) (1%), neutropenia (0.9%), renal impairment (0.9%), AST increased (0.6%), dyspnea (0.6%), pulmonary fibrosis (0.6%) and anemia, rash, weight decreased and thrombocytopenia (each 0.3%).

Dose interruption of VERZENIO due to an adverse reaction occurred in 56% of patients receiving VERZENIO plus anastrozole or letrozole. Adverse reactions leading to VERZENIO dose interruptions in ≥5% of patients were neutropenia (16%) and diarrhea (15%).

Dose reductions due to an adverse reaction occurred in 43% of patients receiving VERZENIO plus anastrozole or letrozole. Adverse reactions leading to dose reductions in ≥5% of patients were diarrhea and neutropenia. VERZENIO dose reductions due to diarrhea of any grade occurred in 13% of patients receiving VERZENIO plus an aromatase inhibitor compared to 2% of patients receiving placebo plus an aromatase inhibitor. VERZENIO dose reductions due to neutropenia of any grade occurred in 11% of patients receiving VERZENIO plus an aromatase inhibitor compared to 0.6% of patients receiving placebo plus an aromatase inhibitor.

The most common adverse reactions reported (≥20%) in the VERZENIO arm and ≥2% than the placebo arm were: diarrhea, neutropenia, fatigue, infections, nausea, abdominal pain, anemia, vomiting, alopecia, decreased appetite, and leukopenia. Adverse reactions are shown in Table 10 and laboratory abnormalities in Table 11. Diarrhea incidence was greatest during the first month of VERZENIO dosing. The median time to onset of the first diarrhea event was 8 days, and the median durations of diarrhea for Grades 2 and for Grade 3 were 11 days and 8 days, respectively. Most diarrhea events recovered or resolved (88%) with supportive treatment and/or dose reductions [see Dosage and Administration (2.2) and Patient Counseling Information (17)]. Nineteen percent of patients with diarrhea required a dose omission and 13% required a dose reduction. The median time to the first dose reduction due to diarrhea was 38 days.

Table 10: Adverse Reactions (≥10%) in Patients Receiving VERZENIO Plus Anastrozole or Letrozole [with a Difference between Arms of ≥2%] in MONARCH 3
 | VERZENIO plus Anastrozole or Letrozole N=327 |  |  | Placebo plus Anastrozole or Letrozole N=161
 | All Grades % | Grade 3 % | Grade 4 % | All Grades % | Grade 3 % | Grade 4 %
Gastrointestinal Disorders
Diarrhea | 81 | 9 | 0 | 30 | 1.2 | 0
Nausea | 39 | 0.9 | 0 | 20 | 1.2 | 0
Abdominal pain | 29 | 1.2 | 0 | 12 | 1.2 | 0
Vomiting | 28 | 1.2 | 0 | 12 | 1.9 | 0
Constipation | 16 | 0.6 | 0 | 12 | 0 | 0
Infections and Infestations
Infectionsa | 39 | 4.0 | 0.9 | 29 | 2.5 | 0.6
General Disorders and Administration Site Conditions
Fatigue | 40 | 1.8 | 0 | 32 | 0 | 0
Influenza like illness | 10 | 0 | 0 | 8 | 0 | 0
Skin and Subcutaneous Tissue Disorders
Alopecia | 27 | 0 | 0 | 11 | 0 | 0
Rash | 14 | 0.9 | 0 | 5 | 0 | 0
Pruritus | 13 | 0 | 0 | 9 | 0 | 0
Metabolism and Nutrition Disorders
Decreased appetite | 24 | 1.2 | 0 | 9 | 0.6 | 0
Investigations
Weight decreased | 10 | 0.6 | 0 | 3.1 | 0.6 | 0
Respiratory, Thoracic, and Mediastinal Disorders
Cough | 13 | 0 | 0 | 9 | 0 | 0
Dyspnea | 12 | 0.6 | 0.3 | 6 | 0.6 | 0
Nervous System Disorders
Dizziness | 11 | 0.3 | 0 | 9 | 0 | 0
a Includes all reported preferred terms that are part of the Infections and Infestations system organ class. Most common infections (>1%) include upper respiratory tract infection, lung infection, and pharyngitis.

Additional adverse reactions in MONARCH 3 include venous thromboembolic events (deep vein thrombosis, pulmonary embolism, and pelvic venous thrombosis), which were reported in 5% of patients treated with VERZENIO plus anastrozole or letrozole as compared to 0.6% of patients treated with anastrozole or letrozole plus placebo.

Table 11: Laboratory Abnormalities (≥10%) in Patients Receiving VERZENIO Plus Anastrozole or Letrozole [with a Difference Between Arms of ≥2%] in MONARCH 3
 | VERZENIO plus Anastrozole or Letrozole N=327 |  |  | Placebo plus Anastrozole or Letrozole N=161
Laboratory Abnormality | All Grades % | Grade 3 % | Grade 4 % | All Grades % | Grade 3 % | Grade 4 %
Creatinine increased | 98 | 2.2 | 0 | 84 | 0 | 0
White blood cell decreased | 82 | 13 | 0 | 27 | 0.6 | 0
Anemia | 82 | 1.6 | 0 | 28 | 0 | 0
Neutrophil count decreased | 80 | 19 | 2.9 | 21 | 2.6 | 0
Lymphocyte count decreased | 53 | 7 | 0.6 | 26 | 1.9 | 0
Platelet count decreased | 36 | 1.3 | 0.6 | 12 | 0.6 | 0
Alanine aminotransferase increased | 48 | 6 | 0.6 | 25 | 1.9 | 0
Aspartate aminotransferase increased | 37 | 3.8 | 0 | 23 | 0.6 | 0

Creatinine Increased

Abemaciclib has been shown to increase serum creatinine due to inhibition of renal tubular secretion transporters, without affecting glomerular function [see Clinical Pharmacology (12.3)]. Across the clinical studies, increases in serum creatinine (mean increase, 0.2-0.3 mg/dL) occurred within the first 28-day cycle of VERZENIO dosing, remained elevated but stable through the treatment period, and were reversible upon treatment discontinuation. Alternative markers such as BUN, cystatin C, or calculated GFR, which are not based on creatinine, may be considered to determine whether renal function is impaired.

MONARCH 2: VERZENIO in Combination with Fulvestrant

Women with HR-positive, HER2-negative advanced or metastatic breast cancer with disease progression on or after prior adjuvant or metastatic endocrine therapy

The safety of VERZENIO (150 mg twice daily) plus fulvestrant (500 mg) versus placebo plus fulvestrant was evaluated in MONARCH 2 [see Clinical Studies (14.2)]. The data described below reflect exposure to VERZENIO in 441 patients with HR-positive, HER2-negative advanced breast cancer who received at least one dose of VERZENIO plus fulvestrant in MONARCH 2.

Median duration of treatment was 12 months for patients receiving VERZENIO plus fulvestrant and 8 months for patients receiving placebo plus fulvestrant.

The most frequently reported (≥5%) Grade 3 or 4 adverse reactions were neutropenia, diarrhea, leukopenia, anemia, and infections.

Deaths during treatment or during the 30-day follow up, regardless of causality, were reported in 18 cases (4%) of VERZENIO plus fulvestrant treated patients versus 10 cases (5%) of placebo plus fulvestrant treated patients. Causes of death for patients receiving VERZENIO plus fulvestrant included: 7 (2%) patient deaths due to underlying disease, 4 (0.9%) due to sepsis, 2 (0.5%) due to pneumonitis, 2 (0.5%) due to hepatotoxicity, and one (0.2%) due to cerebral infarction.

Permanent study treatment discontinuation due to an adverse reaction were reported in 9% of patients receiving VERZENIO plus fulvestrant and in 3% of patients receiving placebo plus fulvestrant. Adverse reactions leading to permanent discontinuation for patients receiving VERZENIO plus fulvestrant were infection (2%), diarrhea (1%), hepatotoxicity (1%), fatigue (0.7%), nausea (0.2%), abdominal pain (0.2%), acute kidney injury (0.2%), and cerebral infarction (0.2%).

Dose interruption of VERZENIO due to an adverse reaction occurred in 52% of patients receiving VERZENIO plus fulvestrant. Adverse reactions leading to VERZENIO dose interruptions in ≥5% of patients were diarrhea (19%) and neutropenia (16%).

Dose reductions due to an adverse reaction occurred in 43% of patients receiving VERZENIO plus fulvestrant. Adverse reactions leading to reductions in ≥5% of patients were diarrhea and neutropenia. VERZENIO dose reductions due to diarrhea of any grade occurred in 19% of patients receiving VERZENIO plus fulvestrant compared to 0.4% of patients receiving placebo and fulvestrant. VERZENIO dose reductions due to neutropenia of any grade occurred in 10% of patients receiving VERZENIO plus fulvestrant compared to no patients receiving placebo plus fulvestrant.

The most common adverse reactions reported (≥20%) in the VERZENIO arm were: diarrhea, fatigue, neutropenia, nausea, infections, abdominal pain, anemia, leukopenia, decreased appetite, vomiting, and headache. Adverse reactions are shown in Table 12 and laboratory abnormalities in Table 13.

Table 12: Adverse Reactions (≥10%) in Patients Receiving VERZENIO Plus Fulvestrant [with a Difference Between Arms of ≥2%] in MONARCH 2
 | VERZENIO plus Fulvestrant N=441 |  |  | Placebo plus Fulvestrant N=223
 | All Grades % | Grade 3 % | Grade 4 % | All Grades % | Grade 3 % | Grade 4 %
Gastrointestinal Disorders
Diarrhea | 86 | 13 | 0 | 25 | 0.4 | 0
Nausea | 45 | 2.7 | 0 | 23 | 0.9 | 0
Abdominal paina | 35 | 2.5 | 0 | 16 | 0.9 | 0
Vomiting | 26 | 0.9 | 0 | 10 | 1.8 | 0
Stomatitis | 15 | 0.5 | 0 | 10 | 0 | 0
Infections and Infestations
Infectionsb | 43 | 5 | 0.7 | 25 | 3.1 | 0.4
General Disorders and Administration Site Conditions
Fatiguec | 46 | 2.7 | 0 | 32 | 0.4 | 0
Edema peripheral | 12 | 0 | 0 | 7 | 0 | 0
Pyrexia | 11 | 0.5 | 0.2 | 6 | 0.4 | 0
Metabolism and Nutrition Disorders
Decreased appetite | 27 | 1.1 | 0 | 12 | 0.4 | 0
Respiratory, Thoracic and Mediastinal Disorders
Cough | 13 | 0 | 0 | 11 | 0 | 0
Skin and Subcutaneous Tissue Disorders
Alopecia | 16 | 0 | 0 | 1.8 | 0 | 0
Pruritus | 13 | 0 | 0 | 6 | 0 | 0
Rash | 11 | 1.1 | 0 | 4.5 | 0 | 0
Nervous System Disorders
Headache | 20 | 0.7 | 0 | 15 | 0.4 | 0
Dysgeusia | 18 | 0 | 0 | 2.7 | 0 | 0
Dizziness | 12 | 0.7 | 0 | 6 | 0 | 0
Investigations
Weight decreased | 10 | 0.2 | 0 | 2.2 | 0.4 | 0
a Includes abdominal pain, abdominal pain upper, abdominal pain lower, abdominal discomfort, abdominal tenderness.
b Includes upper respiratory tract infection, urinary tract infection, lung infection, pharyngitis, conjunctivitis, sinusitis, vaginal infection, sepsis.
c Includes asthenia, fatigue.

Additional adverse reactions in MONARCH 2 include venous thromboembolic events (deep vein thrombosis, pulmonary embolism, cerebral venous sinus thrombosis, subclavian vein thrombosis, axillary vein thrombosis, and DVT inferior vena cava), which were reported in 5% of patients treated with VERZENIO plus fulvestrant as compared to 0.9% of patients treated with fulvestrant plus placebo.

Table 13: Laboratory Abnormalities (≥10%) in Patients Receiving VERZENIO Plus Fulvestrant [with a Difference Between Arms of ≥2%]in MONARCH 2
 | VERZENIO plus Fulvestrant N=441 |  |  | Placebo plus Fulvestrant N=223
 | All Grades % | Grade 3 % | Grade 4 % | All Grades % | Grade 3 % | Grade 4 %
Creatinine increased | 98 | 1.2 | 0 | 74 | 0 | 0
White blood cell decreased | 90 | 23 | 0.7 | 33 | 0.9 | 0
Neutrophil count decreased | 87 | 29 | 3.5 | 30 | 3.7 | 0.5
Anemia | 84 | 2.6 | 0 | 34 | 0.5 | 0
Lymphocyte count decreased | 63 | 12 | 0.2 | 32 | 1.8 | 0
Platelet count decreased | 53 | 0.9 | 1.2 | 15 | 0 | 0
Alanine aminotransferase increased | 41 | 3.9 | 0.7 | 32 | 1.4 | 0
Aspartate aminotransferase increased | 37 | 3.9 | 0 | 25 | 3.7 | 0.5

Creatinine Increased

Abemaciclib has been shown to increase serum creatinine due to inhibition of renal tubular secretion transporters, without affecting glomerular function [see Clinical Pharmacology (12.3)]. In clinical studies, increases in serum creatinine (mean increase, 0.2-0.3 mg/dL) occurred within the first 28-day cycle of VERZENIO dosing, remained elevated but stable through the treatment period, and were reversible upon treatment discontinuation. Alternative markers such as BUN, cystatin C, or calculated glomerular filtration rate (GFR), which are not based on creatinine, may be considered to determine whether renal function is impaired.

MONARCH 1: VERZENIO Administered as a Monotherapy in Metastatic Breast Cancer

Patients with HR-positive, HER2-negative breast cancer who received prior endocrine therapy and 1-2 chemotherapy regimens in the metastatic setting

The safety of VERZENIO was evaluated in MONARCH 1, a single-arm, open-label, multicenter study in 132 women with measurable HR-positive, HER2-negative metastatic breast cancer [see Clinical Studies (14.2)]. Patients received 200 mg VERZENIO orally twice daily until development of progressive disease or unmanageable toxicity. Median duration of treatment was 4.5 months.

The most frequently reported (≥5%) Grade 3 or 4 adverse reactions were diarrhea, neutropenia, fatigue, and leukopenia.

Deaths due to adverse reactions during treatment or during the 30-day follow up were reported in 2% of patients. Cause of death in these patients was due to infection (2 patients) or pneumonitis (1 patient).

Ten patients (8%) discontinued study treatment from adverse reactions due to (1 patient each), abdominal pain, arterial thrombosis, aspartate aminotransferase (AST) increased, blood creatinine increased, chronic kidney disease, diarrhea, ECG QT prolonged, fatigue, hip fracture, and lymphopenia.

Dose interruption of VERZENIO due to an adverse reaction occurred in 58% of patients. The most frequent (≥5%) adverse reactions leading to dose interruptions were diarrhea (24%), neutropenia (16%), fatigue (10%), vomiting (6%), and nausea (5%).

Forty-nine percent of patients had dose reductions due to an adverse reaction. The most frequent adverse reactions that led to dose reductions were diarrhea (20%), neutropenia (11%), and fatigue (9%).

The most common reported adverse reactions (≥20%) were: diarrhea, fatigue, nausea, decreased appetite, abdominal pain, neutropenia, vomiting, infections, anemia, headache, and thrombocytopenia. Adverse reactions are shown in Table 14 and laboratory abnormalities in Table 15.

Table 14: Adverse Reactions (≥10%) of Patients in MONARCH 1
 | VERZENIO N=132
 | All Grades % | Grade 3 % | Grade 4 %
Gastrointestinal Disorders
Diarrhea | 90 | 20 | 0
Nausea | 64 | 4.5 | 0
Abdominal pain | 39 | 2.3 | 0
Vomiting | 35 | 1.5 | 0
Constipation | 17 | 0.8 | 0
Dry mouth | 14 | 0 | 0
Stomatitis | 14 | 0 | 0
Infections and Infestations
Infections | 31 | 4.5 | 0
General Disorders and Administration Site Conditions
Fatiguea | 65 | 13 | 0
Pyrexia | 11 | 0 | 0
Metabolism and Nutrition Disorders
Decreased appetite | 45 | 3.0 | 0
Dehydration | 10 | 2.3 | 0
Respiratory, Thoracic and Mediastinal Disorders
Cough | 19 | 0 | 0
Musculoskeletal and Connective Tissue Disorders
Arthralgia | 15 | 0 | 0
Nervous System Disorders
Headache | 20 | 0 | 0
Dysgeusia | 12 | 0 | 0
Dizziness | 11 | 0 | 0
Skin and Subcutaneous Tissue Disorders
Alopecia | 12 | 0 | 0
Investigations
Weight decreased | 14 | 0 | 0
a Includes asthenia, fatigue.

Table 15: Laboratory Abnormalities for Patients Receiving VERZENIO in MONARCH 1
 | VERZENIO N=132
 | All Grades % | Grade 3 % | Grade 4 %
Creatinine increased | 99 | 0.8 | 0
White blood cell decreased | 91 | 28 | 0
Neutrophil count decreased | 88 | 22 | 4.6
Anemia | 69 | 0 | 0
Lymphocyte count decreased | 42 | 13 | 0.8
Platelet count decreased | 41 | 2.3 | 0
ALT increased | 31 | 3.1 | 0
AST increased | 30 | 3.8 | 0

Creatinine Increased

Abemaciclib has been shown to increase serum creatinine due to inhibition of renal tubular secretion transporters, without affecting glomerular function [see Clinical Pharmacology (12.3)]. In clinical studies, increases in serum creatinine (mean increase, 0.2-0.3 mg/dL) occurred within the first 28-day cycle of VERZENIO dosing, remained elevated but stable through the treatment period, and were reversible upon treatment discontinuation. Alternative markers such as BUN, cystatin C, or calculated GFR, which are not based on creatinine, may be considered to determine whether renal function is impaired.

6.2 Postmarketing Experience

The following adverse reactions have been identified during post-approval use of VERZENIO. Because these reactions are reported voluntarily from a population of uncertain size, it is not always possible to reliably estimate their frequency or establish a causal relationship to drug exposure.

Respiratory disorders: Interstitial lung disease (ILD)/pneumonitis [see Warnings and Precautions (5.3)].

7 DRUG INTERACTIONS

7.1 Effect of Other Drugs on VERZENIO

CYP3A Inhibitors

Strong and moderate CYP3A4 inhibitors increased the exposure of abemaciclib plus its active metabolites to a clinically meaningful extent and may lead to increased toxicity.

Ketoconazole

Avoid concomitant use of ketoconazole. Ketoconazole is predicted to increase the AUC of abemaciclib by up to 16-fold [see Clinical Pharmacology (12.3)].

Other Strong CYP3A Inhibitors

In patients with recommended starting doses of 200 mg twice daily or 150 mg twice daily, reduce the VERZENIO dose to 100 mg twice daily with concomitant use of strong CYP3A inhibitors other than ketoconazole. In patients who have had a dose reduction to 100 mg twice daily due to adverse reactions, further reduce the VERZENIO dose to 50 mg twice daily with concomitant use of strong CYP3A inhibitors. If a patient taking VERZENIO discontinues a strong CYP3A inhibitor, increase the VERZENIO dose (after 3-5 half-lives of the inhibitor) to the dose that was used before starting the inhibitor. Patients should avoid grapefruit products [see Dosage and Administration (2.2) and Clinical Pharmacology (12.3)].

Moderate CYP3A Inhibitors

With concomitant use of moderate CYP3A inhibitors, monitor for adverse reactions and consider reducing the VERZENIO dose in 50 mg decrements as demonstrated in Table 1, if necessary.

Strong and Moderate CYP3A Inducers

Coadministration of strong or moderate CYP3A inducers decreased the plasma concentrations of abemaciclib plus its active metabolites and may lead to reduced activity. Avoid concomitant use of strong or moderate CYP3A inducers and consider alternative agents [see Clinical Pharmacology (12.3)].

8 USE IN SPECIFIC POPULATIONS

8.1 Pregnancy

Risk Summary

Based on findings in animals and its mechanism of action, VERZENIO can cause fetal harm when administered to a pregnant woman [see Clinical Pharmacology (12.1)]. There are no available human data informing the drug-associated risk. Advise pregnant women of the potential risk to a fetus. In animal reproduction studies, administration of abemaciclib during organogenesis was teratogenic and caused decreased fetal weight at maternal exposures that were similar to human clinical exposure based on AUC at the maximum recommended human dose (see Data). Advise pregnant women of the potential risk to a fetus.

The background risk of major birth defects and miscarriage for the indicated population is unknown. However, the background risk in the U.S. general population of major birth defects is 2 to 4% and of miscarriage is 15 to 20% of clinically recognized pregnancies.

Data

Animal Data

In an embryo-fetal development study, pregnant rats received oral doses of abemaciclib up to 15 mg/kg/day during the period of organogenesis. Doses ≥4 mg/kg/day caused decreased fetal body weights and increased incidence of cardiovascular and skeletal malformations and variations. These findings included absent innominate artery and aortic arch, malpositioned subclavian artery, unossified sternebra, bipartite ossification of thoracic centrum, and rudimentary or nodulated ribs. At 4 mg/kg/day in rats, the maternal systemic exposures were approximately equal to the human exposure (AUC) at the recommended dose.

8.2 Lactation

Risk Summary

There are no data on the presence of abemaciclib in human milk, or its effects on the breastfed child or on milk production. Because of the potential for serious adverse reactions in breastfed infants from VERZENIO, advise lactating women not to breastfeed during VERZENIO treatment and for 3 weeks after the last dose.

8.3 Females and Males of Reproductive Potential

Based on animal studies, VERZENIO can cause fetal harm when administered to a pregnant woman [see Use in Specific Populations (8.1)].

Pregnancy Testing

Verify pregnancy status in females of reproductive potential prior to initiating treatment with VERZENIO.

Contraception

Females

Advise females of reproductive potential to use effective contraception during VERZENIO treatment and for 3 weeks after the last dose.

Infertility

Males

Based on findings in animals, VERZENIO may impair fertility in males of reproductive potential [see Nonclinical Toxicology (13.1)].

8.4 Pediatric Use

The safety and effectiveness of VERZENIO have not been established in pediatric patients.

The safety and effectiveness of VERZENIO in combination with chemotherapy was assessed but not established in an open label, dose-finding trial (NCT04238819) in 43 pediatric patients aged 1 to < 17 years with relapsed/refractory solid tumors. No new safety signals were observed in pediatric patients in this study. Abemaciclib exposure in pediatric patients was within the range of the values previously observed in adults given a similar dose per body surface area.

8.5 Geriatric Use

Of the 2791 VERZENIO-treated patients in monarchE, 15% were 65 years of age or older and 2.7% were 75 years of age or older.

Of the 900 patients who received VERZENIO in MONARCH 1, MONARCH 2, and MONARCH 3, 38% were 65 years of age or older and 10% were 75 years of age or older. The most common adverse reactions (≥5%) Grade 3 or 4 in patients ≥65 years of age across MONARCH 1, 2, and 3 were: neutropenia, diarrhea, fatigue, nausea, dehydration, leukopenia, anemia, infections, and ALT increased.

No overall differences in safety or effectiveness of VERZENIO were observed between these patients and younger patients.

8.6 Renal Impairment

No dosage adjustment is required for patients with mild or moderate renal impairment (CLcr ≥30-89 mL/min, estimated by Cockcroft-Gault [C-G]). The pharmacokinetics of abemaciclib in patients with severe renal impairment (CLcr <30 mL/min, C-G), end stage renal disease, or in patients on dialysis is unknown [see Clinical Pharmacology (12.3)].

8.7 Hepatic Impairment

No dosage adjustments are necessary in patients with mild or moderate hepatic impairment (Child-Pugh A or B).

Reduce the dosing frequency when administering VERZENIO to patients with severe hepatic impairment (Child-Pugh C) [see Dosage and Administration (2.2) and Clinical Pharmacology (12.3)].

11 DESCRIPTION

Abemaciclib is a kinase inhibitor for oral administration. It is a white to yellow powder with the empirical formula C27H32F2N8 and a molecular weight 506.59.

The chemical name for abemaciclib is 2-Pyrimidinamine, N-[5-[(4-ethyl-1-piperazinyl)methyl]-2-pyridinyl]-5-fluoro-4-[4-fluoro-2-methyl-1-(1-methylethyl)-1H-benzimidazol-6-yl]-. Abemaciclib has the following structure:

VERZENIO (abemaciclib) tablets are provided as immediate-release oval white, beige, or yellow tablets. Inactive ingredients are as follows: Excipients—microcrystalline cellulose 102, microcrystalline cellulose 101, lactose monohydrate, croscarmellose sodium, sodium stearyl fumarate, silicon dioxide. Color mixture ingredients—polyvinyl alcohol, titanium dioxide, polyethylene glycol, talc, iron oxide yellow, and iron oxide red.

12 CLINICAL PHARMACOLOGY

12.1 Mechanism of Action

Abemaciclib is an inhibitor of cyclin-dependent kinases 4 and 6 (CDK4 and CDK6). These kinases are activated upon binding to D-cyclins. In estrogen receptor-positive (ER+) breast cancer cell lines, cyclin D1 and CDK4/6 promote phosphorylation of the retinoblastoma protein (Rb), cell cycle progression, and cell proliferation. In vitro, continuous exposure to abemaciclib inhibited Rb phosphorylation and blocked progression from G1 into S phase of the cell cycle, resulting in senescence and apoptosis. In breast cancer xenograft models, abemaciclib dosed daily without interruption as a single agent or in combination with antiestrogens resulted in reduction of tumor size.

12.2 Pharmacodynamics

Cardiac Electrophysiology

Based on evaluation of the QTc interval in patients and in a healthy volunteer study, abemaciclib did not cause large mean increases (i.e., 20 ms) in the QTc interval.

12.3 Pharmacokinetics

The pharmacokinetics of abemaciclib were characterized in patients with solid tumors, including breast cancer, and in healthy subjects.

Following single and repeated twice daily dosing of 50 mg (0.3 times the approved recommended 150 mg dosage) to 200 mg of abemaciclib, the increase in plasma exposure (AUC) and Cmax was approximately dose proportional. Steady state was achieved within 5 days following repeated twice daily dosing, and the estimated geometric mean accumulation ratio was 2.3 (50% CV) and 3.2 (59% CV) based on Cmax and AUC, respectively.

Absorption

The absolute bioavailability of abemaciclib after a single oral dose of 200 mg is 45% (19% CV). The median Tmax of abemaciclib is 8.0 hours (range: 4.1-24.0 hours).

Effect of Food

A high-fat, high-calorie meal (approximately 800 to 1000 calories with 150 calories from protein, 250 calories from carbohydrate, and 500 to 600 calories from fat) administered to healthy subjects increased the AUC of abemaciclib plus its active metabolites by 9% and increased Cmax by 26%.

Distribution

In vitro, abemaciclib was bound to human plasma proteins, serum albumin, and alpha-1-acid glycoprotein in a concentration independent manner from 152 ng/mL to 5066 ng/mL. In a clinical study, the mean (standard deviation, SD) bound fraction was 96.3% (1.1) for abemaciclib, 93.4% (1.3) for M2, 96.8% (0.8) for M18, and 97.8% (0.6) for M20. The geometric mean systemic volume of distribution is approximately 690.3 L (49% CV).

In patients with advanced cancer, including breast cancer, concentrations of abemaciclib and its active metabolites M2 and M20 in cerebrospinal fluid are comparable to unbound plasma concentrations.

Elimination

The geometric mean hepatic clearance (CL) of abemaciclib in patients was 26.0 L/h (51% CV), and the mean plasma elimination half-life for abemaciclib in patients was 18.3 hours (72% CV).

Metabolism

Hepatic metabolism is the main route of clearance for abemaciclib. Abemaciclib is metabolized to several metabolites primarily by cytochrome P450 (CYP) 3A4, with formation of N-desethylabemaciclib (M2) representing the major metabolism pathway. Additional metabolites include hydroxyabemaciclib (M20), hydroxy-N-desethylabemaciclib (M18), and an oxidative metabolite (M1). M2, M18, and M20 are equipotent to abemaciclib and their AUCs accounted for 25%, 13%, and 26% of the total circulating analytes in plasma, respectively.

Excretion

After a single 150 mg oral dose of radiolabeled abemaciclib, approximately 81% of the dose was recovered in feces and approximately 3% recovered in urine. The majority of the dose eliminated in feces was metabolites.

Specific Populations

Age, Gender, and Body Weight

Based on a population pharmacokinetic analysis in patients with cancer, age (range 24-91 years), gender (134 males and 856 females), and body weight (range 36-175 kg) had no effect on the exposure of abemaciclib.

Patients with Renal Impairment

In a population pharmacokinetic analysis of 990 individuals, in which 381 individuals had mild renal impairment (60 mL/min ≤ CLcr <90 mL/min) and 126 individuals had moderate renal impairment (30 mL/min ≤ CLcr <60 mL/min), mild and moderate renal impairment had no effect on the exposure of abemaciclib [see Use in Specific Populations (8.6)]. The effect of severe renal impairment (CLcr <30 mL/min) on pharmacokinetics of abemaciclib is unknown.

Patients with Hepatic Impairment

Following a single 200 mg oral dose of abemaciclib, the relative potency adjusted unbound AUC0-INF of abemaciclib plus its active metabolites (M2, M18, M20) in plasma increased 1.2-fold in subjects with mild hepatic impairment (Child-Pugh A, n=9), 1.1-fold in subjects with moderate hepatic impairment (Child-Pugh B, n=10), and 2.4-fold in subjects with severe hepatic impairment (Child-Pugh C, n=6) relative to subjects with normal hepatic function (n=10) [see Use in Specific Populations (8.7)]. In subjects with severe hepatic impairment, the mean plasma elimination half-life of abemaciclib increased to 55 hours compared to 24 hours in subjects with normal hepatic function.

Drug Interaction Studies

Effects of Other Drugs on Abemaciclib

Strong CYP3A Inhibitors: Ketoconazole (a strong CYP3A inhibitor) is predicted to increase the AUC of abemaciclib by up to 16-fold.

Coadministration of 500 mg twice daily doses of clarithromycin (a strong CYP3A inhibitor) with a single 50 mg dose of VERZENIO (0.3 times the approved recommended 150 mg dosage) increased the relative potency adjusted unbound AUC0-INF of abemaciclib plus its active metabolites (M2, M18, and M20) by 2.5-fold relative to abemaciclib alone in cancer patients.

Moderate CYP3A Inhibitors: Verapamil and diltiazem (moderate CYP3A inhibitors) are predicted to increase the relative potency adjusted unbound AUC of abemaciclib plus its active metabolites (M2, M18, and M20) by approximately 1.6-fold and 2.4-fold, respectively.

Strong CYP3A Inducers: Coadministration of 600 mg daily doses of rifampin (a strong CYP3A inducer) with a single 200 mg dose of VERZENIO decreased the relative potency adjusted unbound AUC0-INF of abemaciclib plus its active metabolites (M2, M18, and M20) by approximately 70% in healthy subjects.

Moderate CYP3A Inducers: Efavirenz, bosentan, and modafinil (moderate CYP3A inducers) are predicted to decrease the relative potency adjusted unbound AUC of abemaciclib plus its active metabolites (M2, M18, and M20) by 53%, 41%, and 29%, respectively.

Loperamide: Co-administration of a single 8 mg dose of loperamide with a single 400 mg dose of abemaciclib in healthy subjects increased the relative potency adjusted unbound AUC0-INF of abemaciclib plus its active metabolites (M2 and M20) by 12%, which is not considered clinically relevant.

Endocrine Therapies: In clinical studies in patients with breast cancer, there was no clinically relevant effect of fulvestrant, anastrozole, letrozole, exemestane, or tamoxifen on abemaciclib pharmacokinetics.

Effects of Abemaciclib on Other Drugs

Loperamide: In a clinical drug interaction study in healthy subjects, coadministration of a single 8 mg dose of loperamide with a single 400 mg abemaciclib (2.7 times the approved recommended 150 mg dosage) increased loperamide AUC0-INF by 9% and Cmax by 35% relative to loperamide alone. These increases in loperamide exposure are not considered clinically relevant.

Metformin: In a clinical drug interaction study in healthy subjects, coadministration of a single 1000 mg dose of metformin, a clinically relevant substrate of renal OCT2, MATE1, and MATE2-K transporters, with a single 400 mg dose of abemaciclib (2.7 times the approved recommended 150 mg dosage) increased metformin AUC0-INF by 37% and Cmax by 22% relative to metformin alone. Abemaciclib reduced the renal clearance and renal secretion of metformin by 45% and 62%, respectively, relative to metformin alone, without any effect on glomerular filtration rate (GFR) as measured by iohexol clearance and serum cystatin C.

Endocrine Therapies: In clinical studies in patients with breast cancer, there was no clinically relevant effect of abemaciclib on the pharmacokinetics of fulvestrant, anastrozole, letrozole, exemestane, or tamoxifen.

CYP Metabolic Pathways: In a clinical drug interaction study in patients with cancer, multiple doses of abemaciclib (200 mg twice daily for 7 days) did not result in clinically meaningful changes in the pharmacokinetics of CYP1A2, CYP2C9, CYP2D6 and CYP3A4 substrates. Abemaciclib is a substrate of CYP3A4, and time-dependent changes in pharmacokinetics of abemaciclib as a result of autoinhibition of its metabolism were not observed.

In Vitro Studies

Transporter Systems: Abemaciclib and its major active metabolites inhibit the renal transporters OCT2, MATE1, and MATE2-K at concentrations achievable at the approved recommended dosage. The observed serum creatinine increase in clinical studies with abemaciclib is likely due to inhibition of tubular secretion of creatinine via OCT2, MATE1, and MATE2-K [see Adverse Effects (6.1)]. Abemaciclib and its major metabolites at clinically relevant concentrations do not inhibit the hepatic uptake transporters OCT1, OATP1B1, and OATP1B3 or the renal uptake transporters OAT1 and OAT3.

Abemaciclib is a substrate of P-gp and BCRP. Abemaciclib and its major active metabolites, M2 and M20, are not substrates of hepatic uptake transporters OCT1, organic anion transporting polypeptide 1B1 (OATP1B1), or OATP1B3.

Abemaciclib inhibits P-gp and BCRP. The clinical consequences of this finding on sensitive P-gp and BCRP substrates are unknown.

P-gp and BCRP Inhibitors: In vitro, abemaciclib is a substrate of P-gp and BCRP. The effect of P-gp or BCRP inhibitors on the pharmacokinetics of abemaciclib has not been studied.

13 NONCLINICAL TOXICOLOGY

13.1 Carcinogenesis, Mutagenesis, Impairment of Fertility

Abemaciclib was assessed for carcinogenicity in a 2-year rat study. Abemaciclib was not carcinogenic in male and female rats at oral doses up to 3 mg/kg/day (approximately 1 time the exposure at the maximum recommended human dose based on AUC).

Abemaciclib and its active human metabolites M2 and M20 were not mutagenic in a bacterial reverse mutation (Ames) assay or clastogenic in an in vitro chromosomal aberration assay in Chinese hamster ovary cells or human peripheral blood lymphocytes. Abemaciclib, M2, and M20 were not clastogenic in an in vivo rat bone marrow micronucleus assay.

Abemaciclib may impair fertility in males of reproductive potential. In repeat-dose toxicity studies up to 3-months duration, abemaciclib-related findings in the testis, epididymis, prostate, and seminal vesicle at doses ≥10 mg/kg/day in rats and ≥0.3 mg/kg/day in dogs included decreased organ weights, intratubular cellular debris, hypospermia, tubular dilatation, atrophy, and degeneration/necrosis. These doses in rats and dogs resulted in approximately 2 and 0.02 times, respectively, the exposure (AUC) in humans at the maximum recommended human dose. In a rat male fertility study, abemaciclib had no effects on mating and fertility at oral doses up to 10 mg/kg/day (approximately 2 times the exposure at the maximum recommended human dose based on AUC).

In a rat female fertility and early embryonic development study, abemaciclib did not affect mating and fertility at doses up to 20 mg/kg/day (approximately 3 times the exposure at the maximum recommended human dose based on AUC).

13.2 Animal Toxicology and/or Pharmacology

In repeat-dose toxicity studies up to 6-months duration, oral administration of abemaciclib resulted in retinal atrophy of the eyes in mice at a dose of 150 mg/kg/day (approximately 10 times the exposure at the maximum recommended human dose based on AUC) and in rats at a dose of 30 mg/kg/day (approximately 5 times the exposure at the maximum recommended human dose based on AUC). In a 2-year rat carcinogenicity study, oral administration of abemaciclib resulted in retinal atrophy in the eyes at doses ≥0.3 mg/kg/day (approximately 0.05 times the exposure at the maximum recommended human dose based on AUC).

14 CLINICAL STUDIES

14.1 Early Breast Cancer

VERZENIO in Combination with Standard Endocrine Therapy (monarchE)

Patients with HR-positive, HER2-negative, node-positive early breast cancer at high risk of recurrence

monarchE (NCT03155997) was a randomized (1:1), open-label, two cohort, multicenter study in adult women and men with HR-positive, HER2-negative, node-positive, resected, early breast cancer with clinical and pathological features consistent with a high risk of disease recurrence. To be enrolled, patients had to have HR-positive HER2-negative early breast cancer with tumor involvement in at least 1 axillary lymph node (pALN) and to be enrolled in cohort 1 had to have either:

- ≥4 pALN or
- 1-3 pALN and at least one of:
  - tumor grade 3 or
  - tumor size ≥50 mm

Patients enrolled in cohort 2 could not have met the eligibility criteria for cohort 1. To be enrolled in cohort 2, patients had to have 1-3 pALN and Ki-67 score ≥20%. Breast tumor samples were tested at central sites using the Ki-67 IHC MIB-1 pharmDx (Dako Omnis) assay to establish if the Ki-67 score was ≥20%.

Patients were randomized to receive 2 years of VERZENIO plus physician's choice of standard endocrine therapy or standard endocrine therapy alone. Randomization to treatment was stratified by prior treatment (neoadjuvant chemotherapy versus adjuvant chemotherapy versus no chemotherapy); menopausal status (premenopausal versus postmenopausal); and region (North America/Europe versus Asia versus other). Men were stratified as postmenopausal. After the end of the study treatment period, standard adjuvant endocrine therapy was continued for a duration of at least 5 years if deemed medically appropriate.

The major efficacy outcome measure was invasive disease–free survival (IDFS). IDFS was defined as the time from randomization to the first occurrence of: ipsilateral invasive breast tumor recurrence, regional invasive breast cancer recurrence, distant recurrence, contralateral invasive breast cancer, second primary non-breast invasive cancer, or death attributable to any cause. Overall survival (OS) was an additional outcome measure.

A statistically significant difference in IDFS was observed in the intent-to-treat (ITT) population which was primarily attributed to the patients treated in cohort 1. While the OS data in cohort 2 remains immature, more deaths were observed among those receiving VERZENIO plus standard endocrine therapy compared to those receiving standard endocrine therapy alone (10/253 vs. 5/264).

Of 5637 patients randomized, 5120 (91%) were randomized in cohort 1. Patient median age was 51 years (range, 22-89 years), 99% were women, 70% were White, 24% were Asian, 1.7% were Black or African American, 2.1% were American Indian or Alaska Native, and 0.1% were Native Hawaiian or Other Pacific Islander. Forty-three percent of patients were premenopausal. Most patients received prior chemotherapy (37% neoadjuvant, 59% adjuvant) and prior radiotherapy (96%). Sixty-five percent of the patients had 4 or more positive lymph nodes with 22% having ≥10 positive lymph nodes, 41% had Grade 3 tumor, and 24% had pathological tumor size ≥50 mm. The majority of patients (99%) had estrogen receptor positive disease and 87% had progesterone receptor positive disease. Initial endocrine therapy received by patients included letrozole (39%), tamoxifen (31%), anastrozole (22%), or exemestane (8%).

Efficacy results for cohort 1 are summarized in Table 16 and Figure 1. At the time of OS interim analysis 2, OS was immature and a total of 315 (6%) of patients had died in cohort 1.

Table 16: Efficacy Results in monarchE in Cohort 1
 | VERZENIO Plus Tamoxifen or an Aromatase Inhibitor N=2555 | Tamoxifen or an Aromatase Inhibitor N=2565
Invasive Disease–Free Survival (IDFS)
Number of patients with an event, n (%) | 317 (12) | 474 (18)
Hazard ratio (95% CI) | 0.65 (0.57, 0.75)
IDFS at 48 months, % (95% CI) | 85.5 (83.8, 87.0) | 78.6 (76.7, 80.4)
Abbreviation: CI = confidence interval.

Figure 1: Kaplan-Meier Curves of Invasive Disease–Free Survival VERZENIO plus Tamoxifen or an Aromatase Inhibitor versus Tamoxifen or an Aromatase Inhibitor in Cohort 1 (monarchE)

14.2 Advanced or Metastatic Breast Cancer

VERZENIO in Combination with an Aromatase Inhibitor (Anastrozole or Letrozole) (MONARCH 3)

Postmenopausal women with HR-positive, HER2-negative advanced or metastatic breast cancer with no prior systemic therapy in this disease setting

MONARCH 3 (NCT02246621) was a randomized (2:1), double-blinded, placebo-controlled, multicenter study in postmenopausal women with HR-positive, HER2-negative advanced or metastatic breast cancer in combination with a nonsteroidal aromatase inhibitor as initial endocrine-based therapy, including patients not previously treated with systemic therapy for breast cancer.

Randomization was stratified by disease site (visceral, bone only, or other) and by prior (neo)adjuvant endocrine therapy (aromatase inhibitor versus other versus no prior endocrine therapy). A total of 493 patients were randomized to receive 150 mg VERZENIO or placebo orally twice daily, plus physician's choice of letrozole (80% of patients) or anastrozole (20% of patients). Patient median age was 63 years (range, 32-88 years) and the majority were White (58%) or Asian (30%). A total of 51% had received prior systemic therapy and 39% of patients had received chemotherapy, 53% had visceral disease, and 22% had bone-only disease.

Efficacy results are summarized in Table 17 and Figure 2. PFS was evaluated according to RECIST version 1.1 and PFS assessment based on a blinded independent radiologic review was consistent with the investigator assessment. Consistent PFS results were observed across patient stratification subgroups of disease site and prior (neo)adjuvant endocrine therapy.

Table 17: Efficacy Results in MONARCH 3 (Investigator Assessment, Intent-to-Treat Population)
 | VERZENIO plus Anastrozole or Letrozole | Placebo plus Anastrozole or Letrozole
Progression-Free Survival | N=328 | N=165
Number of patients with an event, n (%) | 138 (42) | 108 (65)
Median in months (95% CI) | 28.2 (23.5, NR) | 14.8 (11.2, 19.2)
Hazard ratio (95% CI) | 0.54 (0.42, 0.70)
p-value | <0.0001
Overall Survival | N=328 | N=165
Number of patients with an event, n (%) | 198 (60) | 116 (70)
Median in months (95% CI) | 66.8 (59.2, 74.8) | 53.7 (44.7, 59.3)
Hazard ratio (95% CI) | 0.80 (0.64, 1.02)
p-value | NS
Objective Response for Patients with Measurable Diseasea | N=267 | N=132
Objective response rate n (%)a,b | 148 (55) | 53 (40)
95% CI | 49, 61 | 32, 49
Abbreviations: CI = confidence interval; OS = overall survival; NR = not reached; NS = not statistically significant.
a Complete response + partial response.
b Based upon confirmed responses.

Figure 2: Kaplan-Meier Curves of Progression-Free Survival: VERZENIO plus Anastrozole or Letrozole versus Placebo plus Anastrozole or Letrozole in Intent-to-Treat Population (MONARCH 3)

VERZENIO in Combination with Fulvestrant (MONARCH 2)

Patients with HR-positive, HER2-negative advanced or metastatic breast cancer with disease progression on or after prior adjuvant or metastatic endocrine therapy

MONARCH 2 (NCT02107703) was a randomized, placebo-controlled, multicenter study in women with HR-positive, HER2-negative metastatic breast cancer in combination with fulvestrant in patients with disease progression following endocrine therapy who had not received chemotherapy in the metastatic setting. Randomization was stratified by disease site (visceral, bone only, or other) and by sensitivity to prior endocrine therapy (primary or secondary resistance). Primary endocrine therapy resistance was defined as relapse while on the first 2 years of adjuvant endocrine therapy or progressive disease within the first 6 months of first line endocrine therapy for metastatic breast cancer. A total of 669 patients were randomized to receive VERZENIO or placebo orally twice daily plus intramuscular injection of 500 mg fulvestrant on days 1 and 15 of cycle 1 and then on day 1 of cycle 2 and beyond (28-day cycles). Pre/perimenopausal women were enrolled in the study and received the gonadotropin-releasing hormone agonist goserelin for at least 4 weeks prior to and for the duration of MONARCH 2. Patients remained on continuous treatment until development of progressive disease or unmanageable toxicity.

Patient median age was 60 years (range, 32-91 years), and 37% of patients were older than 65. The majority were White (56%), and 99% of patients had an Eastern Cooperative Oncology Group (ECOG) performance status of 0 or 1. Twenty percent (20%) of patients had de novo metastatic disease, 27% had bone-only disease, and 56% had visceral disease. Twenty-five percent (25%) of patients had primary endocrine therapy resistance. Seventeen percent (17%) of patients were pre- or perimenopausal.

The efficacy results from the MONARCH 2 study are summarized in Table 18, Figure 3, and Figure 4. PFS assessment based on a blinded independent radiologic review was consistent with the investigator assessment. Consistent results were observed across patient stratification subgroups of disease site and endocrine therapy resistance for PFS and OS.

Table 18: Efficacy Results in MONARCH 2 (Intent-to-Treat Population)
 | VERZENIO plus Fulvestrant | Placebo plus Fulvestrant
Progression-Free Survival (Investigator Assessment) | N=446 | N=223
Number of patients with an event n (%) | 222 (50) | 157 (70)
Median in months (95% CI) | 16.4 (14.4, 19.3) | 9.3 (7.4, 12.7)
Hazard ratio (95% CI)a | 0.55 (0.45, 0.68)
p-valuea | p<.0001
Overall Survivalb
Number of deaths n (%) | 211 (47) | 127 (57)
Median OS in months (95% CI) | 46.7 (39.2, 52.2) | 37.3 (34.4, 43.2)
Hazard ratio (95% CI)a | 0.76 (0.61, 0.95)
p-valuea | p=.0137
Objective Response for Patients with Measurable Disease | N=318 | N=164
Objective response rate n (%)c | 153 (48) | 35 (21)
95% CI | 43, 54 | 15, 28
Abbreviation: CI = confidence interval, OS = overall survival.
a Stratified by disease site (visceral metastases vs. bone-only metastases vs. other) and endocrine therapy resistance (primary resistance vs. secondary resistance)
b Data from a pre-specified interim analysis (77% of the number of events needed for the planned final analysis) with the p-value compared with the allocated alpha of 0.021.
c Complete response + partial response.

Figure 3: Kaplan-Meier Curves of Progression-Free Survival: VERZENIO plus Fulvestrant versus Placebo plus Fulvestrant (MONARCH 2)

Figure 4: Kaplan-Meier Curves of Overall Survival: VERZENIO plus Fulvestrant versus Placebo plus Fulvestrant (MONARCH 2)

VERZENIO Administered as a Monotherapy in Metastatic Breast Cancer (MONARCH 1)

Patients with HR-positive, HER2-negative breast cancer who received prior endocrine therapy and 1-2 chemotherapy regimens in the metastatic setting

MONARCH 1 (NCT02102490) was a single-arm, open-label, multicenter study in women with measurable HR-positive, HER2-negative metastatic breast cancer whose disease progressed during or after endocrine therapy, had received a taxane in any setting, and who received 1 or 2 prior chemotherapy regimens in the metastatic setting. A total of 132 patients received 200 mg VERZENIO orally twice daily on a continuous schedule until development of progressive disease or unmanageable toxicity.

Patient median age was 58 years (range, 36-89 years), and the majority of patients were White (85%). Patients had an Eastern Cooperative Oncology Group performance status of 0 (55% of patients) or 1 (45%). The median duration of metastatic disease was 27.6 months. Ninety percent (90%) of patients had visceral metastases, and 51% of patients had 3 or more sites of metastatic disease. Fifty-one percent (51%) of patients had had one line of chemotherapy in the metastatic setting. Sixty-nine percent (69%) of patients had received a taxane-based regimen in the metastatic setting and 55% had received capecitabine in the metastatic setting. Table 19 provides the efficacy results from MONARCH 1.

Table 19: Efficacy Results in MONARCH 1 (Intent-to-Treat Population)
 | VERZENIO 200 mg N=132
 | Investigator Assessed | Independent Review
Objective Response Ratea,b, n (%) | 26 (20) | 23 (17)
95% CI | 13, 28 | 11, 25
Median Duration of Response in months | 8.6 | 7.2
95% CI | 5.8, 10.2 | 5.6, NR
Abbreviations: CI = confidence interval, NR = not reached.
a All responses were partial responses.
b Based upon confirmed responses.

16 HOW SUPPLIED/STORAGE AND HANDLING

How Supplied

VERZENIO 50 mg tablets are oval beige tablet with “Lilly” debossed on one side and “50” on the other side.

VERZENIO 100 mg tablet are oval white to practically white tablet with “Lilly” debossed on one side and “100” on the other side.

VERZENIO 150 mg tablets are oval yellow tablet with “Lilly” debossed on one side and “150” on the other side.

VERZENIO 200 mg tablets are oval beige tablet with “Lilly” debossed on one side and “200” on the other side.

VERZENIO tablets are supplied in 7-day dose pack configurations as follows:

- 200 mg dose pack (14 tablets) – each blister pack contains 14 tablets (200 mg per tablet) (200 mg twice daily)

NDC 0002-6216-54

- 150 mg dose pack (14 tablets) – each blister pack contains 14 tablets (150 mg per tablet) (150 mg twice daily)

NDC 0002-5337-54

- 100 mg dose pack (14 tablets) – each blister pack contains 14 tablets (100 mg per tablet) (100 mg twice daily)

NDC 0002-4815-54

- 50 mg dose pack (14 tablets) – each blister pack contains 14 tablets (50 mg per tablet) (50 mg twice daily)

NDC 0002-4483-54

Storage and Handling

Store at 20°C to 25°C (68°F to 77°F); excursions permitted to 15°C to 30°C (59°F to 86°F).

17 PATIENT COUNSELING INFORMATION

Advise the patient to read the FDA-approved patient labeling (Patient Information).

Diarrhea

VERZENIO may cause diarrhea, which may be severe in some cases [see Warnings and Precautions (5.1)].

- Early identification and intervention is critical for the optimal management of diarrhea. Instruct patients that at the first sign of loose stools, they should start antidiarrheal therapy (for example, loperamide) and notify their healthcare provider for further instructions and appropriate follow up.
- Encourage patients to increase oral fluids.
- If diarrhea does not resolve with antidiarrheal therapy within 24 hours to ≤Grade 1, suspend VERZENIO dosing [see Dosage and Administration (2.2)].

Neutropenia

Advise patients of the possibility of developing neutropenia and to immediately contact their healthcare provider should they develop a fever, particularly in association with any signs of infection [see Warnings and Precautions (5.2)].

Interstitial Lung Disease/Pneumonitis

Advise patients to immediately report new or worsening respiratory symptoms [see Warnings and Precautions (5.3)].

Hepatotoxicity

Inform patients of the signs and symptoms of hepatotoxicity. Advise patients to contact their healthcare provider immediately for signs or symptoms of hepatotoxicity [see Warnings and Precautions (5.4)].

Venous Thromboembolism

Advise patients to immediately report any signs or symptoms of thromboembolism such as pain or swelling in an extremity, shortness of breath, chest pain, tachypnea, and tachycardia [see Warnings and Precautions (5.5)].

Embryo-Fetal Toxicity

- Advise pregnant women and females of reproductive potential of the potential risk to a fetus. Advise females to inform their healthcare provider of a known or suspected pregnancy [see Warnings and Precautions (5.6) and Use in Specific Populations (8.1)].
- Advise females of reproductive potential to use effective contraception during VERZENIO treatment and for 3 weeks after the last dose [see Use in Specific Populations (8.1, 8.3)].

Lactation

Advise lactating women not to breastfeed during VERZENIO treatment and for at least 3 weeks after the last dose [see Use in Specific Populations (8.2)].

Infertility

Inform males of reproductive potential that VERZENIO may impair fertility [see Use in Specific Populations (8.3)].

Drug Interactions

- Inform patients to avoid concomitant use of ketoconazole. Dose reduction may be required for other strong CYP3A inhibitors or for moderate CYP3A inhibitors [see Dosage and Administration (2.2) and Drug Interactions (7)].
- Grapefruit may interact with VERZENIO. Advise patients not to consume grapefruit products while on treatment with VERZENIO.
- Advise patients to avoid concomitant use of strong and moderate CYP3A inducers and to consider alternative agents [see Dosage and Administration (2.2) and Drug Interactions (7)].
- Advise patients to inform their healthcare providers of all concomitant medications, including prescription medicines, over-the-counter drugs, vitamins, and herbal products [see Dosage and Administration (2.2) and Drug Interactions (7)].

Dosing

- Instruct patients to take the doses of VERZENIO at approximately the same times every day and to swallow whole (do not chew, crush, or split them prior to swallowing) [see Dosage and Administration (2.1)].
- If patient vomits or misses a dose, advise the patient to take the next prescribed dose at the usual time [see Dosage and Administration (2.1)].
- Advise the patient that VERZENIO may be taken with or without food [see Dosage and Administration 2.1)].

Marketed by: Lilly USA, LLC, Indianapolis, IN 46285, USA

Copyright © 2017, 2025, Eli Lilly and Company. All rights reserved.

VER-0010-USPI-20250227

PATIENT INFORMATION
VERZENIO® (ver-ZEN-ee-oh)
(abemaciclib)
tablets

What is the most important information I should know about VERZENIO?
VERZENIO may cause serious side effects including:

- Diarrhea. Diarrhea is common with VERZENIO treatment and may sometimes be severe. Diarrhea may cause you to develop dehydration or an infection. The most common time to develop diarrhea is during the first month of VERZENIO treatment. If you develop diarrhea during treatment with VERZENIO, your healthcare provider may tell you to temporarily stop taking VERZENIO, stop your treatment, or decrease your dose.
  - If you have any loose stools, start taking an antidiarrheal medicine (such as loperamide), drink more fluids, and tell your healthcare provider right away.
- Low white blood cell counts (neutropenia). Low white blood cell counts are common during treatment with VERZENIO and may cause serious infections that can lead to death. Your healthcare provider should check your white blood cell counts before and during treatment. If you develop low white blood cell counts during treatment with VERZENIO, your healthcare provider may tell you to temporarily stop taking VERZENIO, decrease your dose, or wait before starting your next month of treatment. Tell your healthcare provider right away if you have signs and symptoms of low white blood cell counts or infections, such as fever and chills.
- Lung problems. VERZENIO may cause severe or life-threatening inflammation of the lungs during treatment that can lead to death. If you develop lung problems during treatment with VERZENIO, your healthcare provider may tell you to temporarily stop taking VERZENIO, decrease your dose, or stop your treatment. Tell your healthcare provider right away if you have any new or worsening symptoms, including:
  - trouble breathing or shortness of breath
  - cough with or without mucus
  - chest pain
- Liver problems. VERZENIO can cause serious liver problems. Your healthcare provider should do blood tests to check your liver before and during treatment with VERZENIO. If you develop liver problems during treatment with VERZENIO, your healthcare provider may reduce your dose or stop your treatment. Tell your healthcare provider right away if you have any of the following signs and symptoms of liver problems:

- feeling very tired
- pain on the upper right side of your stomach area (abdomen)

- loss of appetite
- bleeding or bruising more easily than normal

- Blood clots in your veins, or in the arteries of your lungs. VERZENIO may cause serious blood clots that have led to death. If you develop blood clots during treatment with VERZENIO, your healthcare provider may tell you to temporarily stop taking VERZENIO. Tell your healthcare provider right away if you get any of the following signs and symptoms of a blood clot:

- pain or swelling in your arms or legs
- shortness of breath
- chest pain

- rapid breathing
- rapid heart rate

See “What are the possible side effects of VERZENIO?” for more information about side effects.

What is VERZENIO?
VERZENIO is a prescription medicine used:

- in combination with endocrine therapy (tamoxifen or an aromatase inhibitor) to treat adults with hormone receptor (HR)-positive, human epidermal growth factor receptor 2 (HER2)-negative, node-positive, early breast cancer with a high risk of coming back as determined by your healthcare provider.
- in combination with an aromatase inhibitor as the first endocrine-based therapy to treat adults with hormone receptor (HR)-positive, human epidermal growth factor receptor 2 (HER2)-negative breast cancer that has worsened or that has spread to other parts of the body (metastatic).
- in combination with fulvestrant to treat adults with hormone receptor (HR)-positive, human epidermal growth factor receptor 2 (HER2)-negative breast cancer that has worsened or spread to other parts of the body (metastatic) and whose disease has progressed after endocrine therapy.
- alone to treat adults with HR-positive, HER2-negative breast cancer that has worsened or that has spread to other parts of the body (metastatic) and whose disease has progressed after endocrine therapy and prior chemotherapy.

When VERZENIO is used in combination with fulvestrant, tamoxifen, or an aromatase inhibitor, also read the Patient Information for the prescribed product. Ask your healthcare provider if you are not sure.
It is not known if VERZENIO is safe and effective in children.

Before taking VERZENIO, tell your healthcare provider about all of your medical conditions, including if you:

- have fever, chills, or any other signs of an infection.
- have a history of blood clots in your veins.
- have lung or breathing problems.
- have liver or kidney problems.
- are pregnant or plan to become pregnant. VERZENIO can harm your unborn baby.
  Females who are able to become pregnant:
  - Your healthcare provider will do a pregnancy test before you start treatment with VERZENIO.
  - You should use effective birth control (contraception) during treatment with VERZENIO and for 3 weeks after the last dose of VERZENIO.
  - Tell your healthcare provider right away if you become pregnant or think you are pregnant during treatment with VERZENIO.
- are breastfeeding or plan to breastfeed. It is not known if VERZENIO passes into your breast milk. Do not breastfeed during treatment with VERZENIO and for at least 3 weeks after the last dose of VERZENIO.

Tell your healthcare provider about all the medicines you take, including prescription and over-the-counter medicines, vitamins, and herbal supplements. VERZENIO may affect the way other medicines work, and other medicines may affect how VERZENIO works, causing serious side effects.
Especially tell your healthcare provider if you take a medicine that contains ketoconazole.
Know the medicines you take. Keep a list of them to show your healthcare provider or pharmacist when you get a new medicine.

How should I take VERZENIO?

- Take VERZENIO exactly as your healthcare provider tells you.
- Your healthcare provider may change your dose if needed. Do not stop taking VERZENIO or change the dose without talking to your healthcare provider.
- VERZENIO may be taken with or without food.
- Swallow VERZENIO tablets whole. Do not chew, crush, or split the tablets before swallowing. Do not take VERZENIO tablets if they are broken, cracked, or damaged.
- Take your doses of VERZENIO at about the same time every day.
- If you vomit or miss a dose of VERZENIO, take your next dose at your regular time. Do not take 2 doses of VERZENIO at the same time to make up for the missed dose.

What should I avoid during treatment with VERZENIO?

- Avoid taking ketoconazole during treatment with VERZENIO. Tell your healthcare provider if you take a medicine that contains ketoconazole.
- Avoid grapefruit and products that contain grapefruit during treatment with VERZENIO. Grapefruit may increase the amount of VERZENIO in your blood.

What are the possible side effects of VERZENIO?
VERZENIO may cause serious side effects, including:

- See “What is the most important information I should know about VERZENIO?”

The most common side effects of VERZENIO include:

- nausea
- infections
- low red blood cell counts (anemia)
- decreased appetite
- headache
- hair thinning or hair loss (alopecia)

- abdominal pain
- tiredness
- low white blood cell counts (leukopenia)
- vomiting
- low platelet count (thrombocytopenia)

VERZENIO may cause fertility problems in males. This may affect your ability to father a child. Talk to your healthcare provider if this is a concern for you.
These are not all the possible side effects of VERZENIO. For more information, ask your healthcare provider or pharmacist.
Call your healthcare provider for medical advice about side effects. You may report side effects to FDA at 1-800-FDA-1088.

How should I store VERZENIO?

- Store VERZENIO at room temperature between 68°F to 77°F (20°C to 25°C).

Keep VERZENIO and all medicines out of the reach of children.

General information about the safe and effective use of VERZENIO.
Medicines are sometimes prescribed for purposes other than those listed in a Patient Information leaflet. Do not use VERZENIO for a condition for which it was not prescribed. Do not give VERZENIO to other people, even if they have the same symptoms you have. It may harm them. You can ask your pharmacist or healthcare provider for more information about VERZENIO that is written for health professionals.

What are the ingredients in VERZENIO?
Active ingredient: abemaciclib
Inactive ingredients: microcrystalline cellulose 102, microcrystalline cellulose 101, lactose monohydrate, croscarmellose sodium, sodium stearyl fumarate, silicon dioxide.
Color mixture ingredients: polyvinyl alcohol, titanium dioxide, polyethylene glycol, talc, iron oxide yellow, iron oxide red.
Marketed by: Lilly USA, LLC, Indianapolis, IN 46285, USA
Copyright © 2017, 2023, Eli Lilly and Company. All rights reserved.
VER-0005-PPI-20230303
For more information, go to www.verzenio.com or call 1-800-545-5979.

This Patient Information has been approved by the U.S. Food and Drug Administration.

Revised: March-2023

PACKAGE CARTON – VERZENIO 50 mg 14ct

14 tablets

NDC 0002-4483-54

Rx only

Verzenio®

(abemaciclib) tablets

50 mg dose

7-Day Supply

This 50 mg Dose Pack contains fourteen 50 mg tablets.

www.verzenio.com

LIFT TO OPEN

Lilly

PACKAGE CARTON – VERZENIO 100 mg 14ct

14 tablets

NDC 0002-4815-54

Rx only

Verzenio®

(abemaciclib) tablets

100 mg dose

7-Day Supply

This 100 mg Dose Pack contains fourteen 100 mg tablets.

www.verzenio.com

LIFT TO OPEN

Lilly

PACKAGE CARTON – VERZENIO 150 mg 14ct

14 tablets

NDC 0002-5337-54

Rx only

Verzenio®

(abemaciclib) tablets

150 mg dose

7-Day Supply

This 150 mg Dose Pack contains fourteen 150 mg tablets.

www.verzenio.com

LIFT TO OPEN

Lilly

PACKAGE CARTON – VERZENIO 200 mg 14ct

14 tablets

NDC 0002-6216-54

Rx only

Verzenio®

(abemaciclib) tablets

200 mg dose

7-Day Supply

This 200 mg Dose Pack contains fourteen 200 mg tablets.

www.verzenio.com

LIFT TO OPEN

Lilly